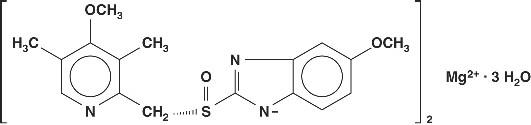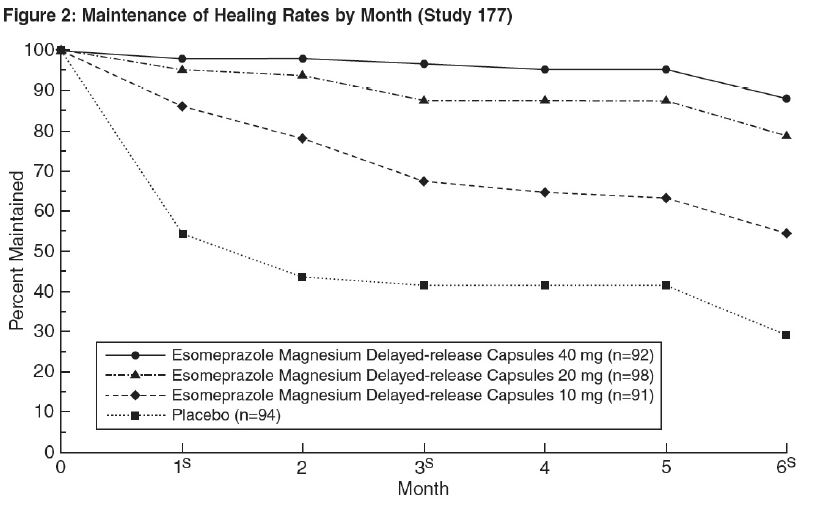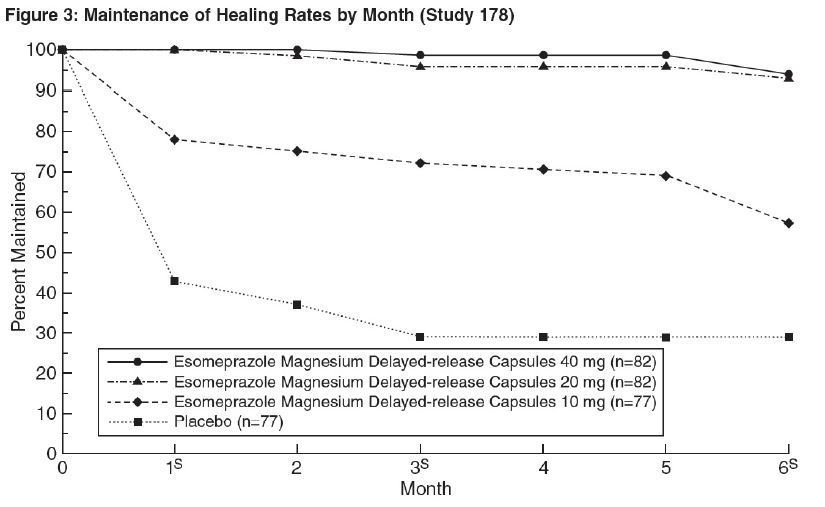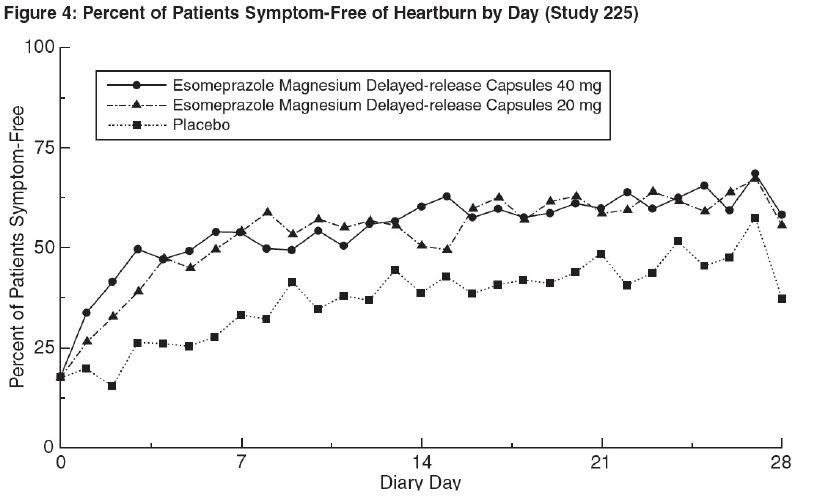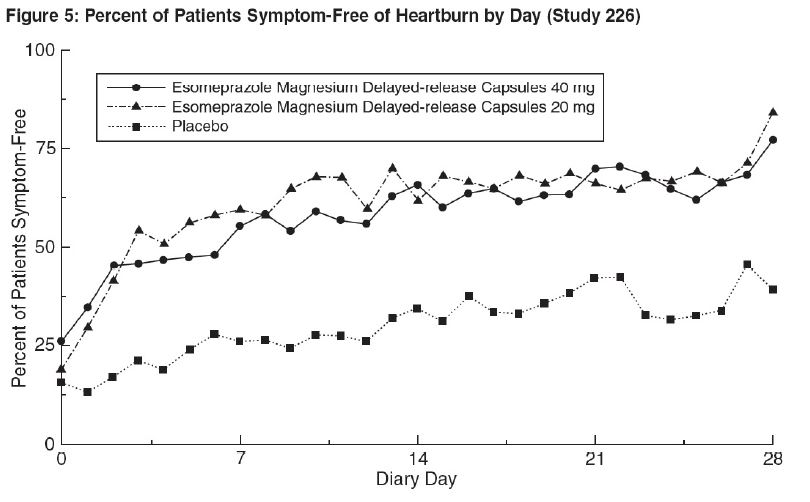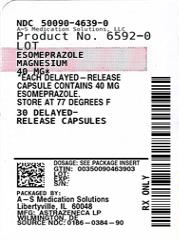 DRUG LABEL: Esomeprazole magnesium
NDC: 50090-4639 | Form: CAPSULE, DELAYED RELEASE
Manufacturer: A-S Medication Solutions
Category: prescription | Type: HUMAN PRESCRIPTION DRUG LABEL
Date: 20210415

ACTIVE INGREDIENTS: ESOMEPRAZOLE MAGNESIUM 40 mg/1 1
INACTIVE INGREDIENTS: GLYCERYL MONOSTEARATE; HYDROXYPROPYL CELLULOSE (1600000 WAMW); HYPROMELLOSE, UNSPECIFIED; MAGNESIUM STEARATE; METHACRYLIC ACID; TALC; TRIETHYL CITRATE; POLYSORBATE 80; GELATIN, UNSPECIFIED; FD&C BLUE NO. 1; FD&C RED NO. 40; TITANIUM DIOXIDE; ALCOHOL; ISOPROPYL ALCOHOL; BUTYL ALCOHOL; POLYETHYLENE GLYCOL, UNSPECIFIED; SODIUM HYDROXIDE; POVIDONE, UNSPECIFIED

HIGHLIGHTS OF PRESCRIBING INFORMATION

These highlights do not include all the information needed to use esomeprazole magnesium delayed-release capsules safely and effectively. See full prescribing information for esomeprazole magnesium delayed-release capsules.
ESOMEPRAZOLE MAGNESIUM delayed-release capsules, for oral use
Initial U.S. Approval: 1989 (omeprazole)

RECENT MAJOR CHANGES

Warnings and Precautions, Acute Tubulointerstitial Nephritis (5.2) 11/2020

1 INDICATIONS AND USAGE

Esomeprazole magnesium is a proton pump inhibitor indicated for the following:

- Treatment of gastroesophageal reflux disease (GERD). (1.1)
- Risk reduction of NSAID-associated gastric ulcer. (1.2)
- H. pylori eradication to reduce the risk of duodenal ulcer recurrence. (1.3)
- Pathological hypersecretory conditions, including Zollinger-Ellison syndrome. (1.4)

2 DOSAGE AND ADMINISTRATION

Indication | Dose | Frequency
Gastroesophageal Reflux Disease (GERD)
Adults | 20 mg or 40 mg | Once daily for 4 to 8 weeks
12 to 17 years | 20 mg or 40 mg | Once daily for up to 8 weeks
1 to 11 years | 10 mg or 20 mg | Once daily for up to 8 weeks
1 month to less than 1 year: 2.5 mg, 5 mg or 10 mg (based on weight). Once daily, up to 6 weeks for erosive esophagitis (EE) due to acid-mediated GERD only.
Risk Reduction of NSAID-Associated Gastric Ulcer
 | 20 mg or 40 mg | Once daily for up to 6 months
H. pylori Eradication (Triple Therapy):
Esomeprazole magnesium; delayed-release capsules | 40 mg | Once daily for 10 days
Amoxicillin | 1000 mg | Twice daily for 10 days
Clarithromycin | 500 mg | Twice daily for 10 days
Pathological Hypersecretory Conditions
 | 40 mg | Twice daily

See full prescribing information for administration options. (2)

Patients with severe liver impairment-do not exceed dose of 20 mg. (2)

3 DOSAGE FORMS AND STRENGTHS

- ESOMEPRAZOLE MAGNESIUM delayed-release capsules: 20 mg and 40 mg. (3)

4 CONTRAINDICATIONS

Patients with known hypersensitivity to proton pump inhibitors (PPIs) (angioedema and anaphylaxis have occurred). (4)

5 WARNINGS AND PRECAUTIONS

- Gastric Malignancy: In adults, symptomatic response does not preclude the presence of gastric malignancy. Consider additional follow-up and diagnostic testing. (5.1)
- Acute Tubulointerstitial Nephritis: Discontinue treatment and evaluate patients. (5.2)
- Clostridium difficile-Associated Diarrhea: PPI therapy may be associated with increased risk. (5.3)
- Bone Fracture: Long-term and multiple daily dose PPI therapy may be associated with an increased risk for osteoporosis-related fractures of the hip, wrist or spine. (5.4)
- Cutaneous and Systemic Lupus Erythematosus: Mostly cutaneous; new onset or exacerbation of existing disease; discontinue esomeprazole magnesium and refer to specialist for evaluation. (5.5)
- Interaction with Clopidogrel: Avoid concomitant use of esomeprazole magnesium. (5.6)
- Cyanocobalamin (Vitamin B-12) Deficiency: Daily long-term use (e.g., longer than 3 years) may lead to malabsorption or a deficiency of cyanocobalamin. (5.7)
- Hypomagnesemia: Reported rarely with prolonged treatment with PPIs. (5.8)
- Interaction with St. John’s Wort or Rifampin: Avoid concomitant use of esomeprazole magnesium. (5.9, 7.3)
- Interactions with Diagnostic Investigations for Neuroendocrine Tumors: Increased chromogranin A (CgA) levels may interfere with diagnostic investigations for neuroendocrine tumors, temporarily stop esomeprazole magnesium at least 14 days before assessing CgA levels. (5.10, 12.2)
- Interaction with Methotrexate: Concomitant use with PPIs may elevate and/or prolong serum concentrations of methotrexate and/or its metabolite, possibly leading to toxicity. With high dose methotrexate administration, consider temporary withdrawal of esomeprazole magnesium. (5.11, 7.7)
- Fundic Gland Polyps: Risk increases with long-term use, especially beyond one year. Use the shortest duration of therapy. (5.12)

6 ADVERSE REACTIONS

Most common adverse reactions (6.1):

- Adults (≥ 18 years) (incidence >1%) are headache, diarrhea, nausea, flatulence, abdominal pain, constipation, and dry mouth.
- Pediatric (1 to 17 years) (incidence ≥2%) are headache, diarrhea, abdominal pain, nausea, and somnolence.
- Pediatric (1 month to less than 1 year) (incidence 1%) are abdominal pain, regurgitation, tachypnea, and increased ALT.

To report SUSPECTED ADVERSE REACTIONS, contact AstraZeneca at 1-800-236-9933 or FDA at 1-800-FDA-1088 or www.fda.gov/medwatch.

7 DRUG INTERACTIONS

- May affect plasma levels of antiretroviral drugs – use with atazanavir and nelfinavir is not recommended; if saquinavir is used with esomeprazole magnesium, monitor for toxicity and consider saquinavir dose reduction. (7.1)
- May interfere with drugs for which gastric pH affects bioavailability (e.g., ketoconazole, iron salts, erlotinib, digoxin and mycophenolate mofetil). Patients treated with esomeprazole magnesium and digoxin may need to be monitored for digoxin toxicity. (7.2)
- Combined inhibitor of CYP2C19 and 3A4 may raise esomeprazole levels. (7.3)
- Clopidogrel: esomeprazole magnesium decreases exposure to the active metabolite of clopidogrel. (7.3)
- May increase systemic exposure of cilostazol and an active metabolite. Consider dose reduction. (7.3)
- Tacrolimus: esomeprazole magnesium may increase serum levels of tacrolimus. (7.5)
- Methotrexate: esomeprazole magnesium may increase serum levels of methotrexate. (7.7)

FULL PRESCRIBING INFORMATION

1 INDICATIONS AND USAGE

1.1 Treatment of Gastroesophageal Reflux Disease (GERD)

Healing of Erosive Esophagitis

Esomeprazole magnesium delayed-release capsules are indicated for the short-term treatment (4 to 8 weeks) in the healing and symptomatic resolution of diagnostically confirmed erosive esophagitis. For those patients who have not healed after 4 to 8 weeks of treatment, an additional 4 to 8 week course of esomeprazole magnesium delayed-release capsules may be considered.

In infants 1 month to less than 1 year, esomeprazole magnesium delayed-release capsules are indicated for short-term treatment (up to 6 weeks) of erosive esophagitis due to acid-mediated GERD.

Maintenance of Healing of Erosive Esophagitis

Esomeprazole magnesium delayed-release capsules are indicated to maintain symptom resolution and healing of erosive esophagitis. Controlled studies do not extend beyond 6 months.

Symptomatic Gastroesophageal Reflux Disease

Esomeprazole magnesium delayed-release capsules are indicated for short-term treatment (4 to 8 weeks) of heartburn and other symptoms associated with GERD in adults and children 1 year or older.

1.2 Risk Reduction of NSAID-Associated Gastric Ulcer

Esomeprazole magnesium delayed-release capsules are indicated for the reduction in the occurrence of gastric ulcers associated with continuous NSAID therapy in patients at risk for developing gastric ulcers. Patients are considered to be at risk due to their age (≥ 60) and/or documented history of gastric ulcers. Controlled studies do not extend beyond 6 months.

1.3 H. pylori Eradication to Reduce the Risk of Duodenal Ulcer Recurrence

Triple Therapy (esomeprazole magnesium plus amoxicillin and clarithromycin): esomeprazole magnesium delayed-release capsules, in combination with amoxicillin and clarithromycin, are indicated for the treatment of patients with H. pylori infection and duodenal ulcer disease (active or history of within the past 5 years) to eradicate H. pylori. Eradication of H. pylori has been shown to reduce the risk of duodenal ulcer recurrence [see Dosage and Administration (2) and Clinical Studies (14)].

In patients who fail therapy, susceptibility testing should be done. If resistance to clarithromycin is demonstrated or susceptibility testing is not possible, alternative antimicrobial therapy should be instituted [see Clinical Pharmacology (12.4) and the prescribing information for clarithromycin].

1.4 Pathological Hypersecretory Conditions Including Zollinger-Ellison Syndrome

Esomeprazole magnesium delayed-release capsules are indicated for the long-term treatment of pathological hypersecretory conditions, including Zollinger-Ellison Syndrome.

2 DOSAGE AND ADMINISTRATION

Esomeprazole magnesium delayed-release capsules are supplied as delayed-release capsules for oral administration. The recommended dosages are outlined in Table 1. Esomeprazole magnesium delayed-release capsules should be taken at least one hour before meals.

The duration of proton pump inhibitor administration should be based on available safety and efficacy data specific to the defined indication and dosing frequency, as described in the prescribing information, and individual patient medical needs. Proton pump inhibitor treatment should only be initiated and continued if the benefits outweigh the risks of treatment.

Table 1: Recommended Dosage Schedule for Esomeprazole Magnesium Delayed-Release Capsules
Indication |  | Dose | Frequency
Gastroesophageal Reflux Disease (GERD)
Healing of Erosive Esophagitis | 20 mg or 40 mg |  | Once Daily for 4 to 8 Weeks [[See Clinical Studies (14.1)] The majority of patients are healed within 4 to 8 weeks. For patients who do not heal after 4 to 8 weeks, an additional 4 to 8 weeks of treatment may be considered.]
Maintenance of Healing of Erosive Esophagitis | 20 mg |  | Once Daily [Controlled studies did not extend beyond six months.]
Symptomatic Gastroesophageal Reflux Disease | 20 mg |  | Once Daily for 4 Weeks [If symptoms do not resolve completely after 4 weeks, an additional 4 weeks of treatment may be considered.]
Pediatric GERD
12 to 17 Year Olds
Healing of Erosive Esophagitis Symptomatic GERD | 20 mg or 40 mg; 20 mg |  | Once Daily for 4 to 8 Weeks; Once Daily for 4 Weeks
1 to 11 Year Olds [Doses over 1 mg/kg/day have not been studied.]
Short-term Treatment of Symptomatic GERD | 10 mg |  | Once Daily for up to 8 Weeks
Healing of Erosive Esophagitis
weight < 20 kg | 10 mg |  | Once Daily for 8 Weeks
weight ≥ 20 kg | 10 mg or 20 mg |  | Once Daily for 8 Weeks
1 month to < 1 year old [Doses over 1.33 mg/kg/day have not been studied.]
Erosive Esophagitis due to acid-mediated GERD
weight 3 kg to 5 kg | 2.5 mg |  | Once Daily for up to 6 Weeks
weight > 5 kg to 7.5 kg | 5 mg |  | Once Daily for up to 6 Weeks
weight >7.5 kg to 12 kg | 10 mg |  | Once Daily for up to 6 Weeks
Risk Reduction of NSAID-Associated Gastric Ulcer | 20 mg or 40 mg |  | Once Daily for up to 6 months
H. pylori Eradication to Reduce the Risk of Duodenal Ulcer Recurrence
Triple Therapy:
Esomeprazole Magnesium Delayed-Release Capsules |  | 40 mg | Once Daily for 10 Days
Amoxicillin |  | 1000 mg | Twice Daily for 10 Days
Clarithromycin |  | 500 mg | Twice Daily for 10 Days
Pathological Hypersecretory Conditions Including Zollinger-Ellison Syndrome |  | 40 mg [The dosage of esomeprazole magnesium delayed-release capsules in patients with pathological hypersecretory conditions varies with the individual patient. Dosage regimens should be adjusted to individual patient needs.] | Twice Daily [Doses up to 240 mg daily have been administered [see Drug Interactions (7)].]

Please refer to amoxicillin and clarithromycin prescribing information for Contraindications, Warnings, and dosing in elderly and renally-impaired patients.

Specific Populations

Hepatic Insufficiency

In patients with mild to moderate liver impairment (Child-Pugh Classes A and B), no dosage adjustment is necessary. For patients with severe liver impairment (Child-Pugh Class C), a dose of 20 mg of esomeprazole magnesium delayed-release capsules should not be exceeded [see Clinical Pharmacology (12.3)].

Directions for use specific to the route and available methods of administration for each of these dosage forms are presented in Table 2.

Table 2: Administration Options
Administration Options
(See text following table for additional instructions.)
Dosage Form | Route | Options
Delayed-Release Capsules | Oral | Capsule can be swallowed whole.; -or-; Capsule can be opened and mixed with applesauce.
Delayed-Release Capsules | Nasogastric Tube | Capsule can be opened and the intact granules emptied into a syringe and delivered through the nasogastric tube.

Esomeprazole magnesium delayed-release capsules

Esomeprazole magnesium delayed-release capsules should be swallowed whole.

Alternatively, for patients who have difficulty swallowing capsules, one tablespoon of applesauce can be added to an empty bowl and the esomeprazole magnesium delayed-release capsules can be opened, and the granules inside the capsule carefully emptied onto the applesauce. The granules should be mixed with the applesauce and then swallowed immediately: do not store for future use. The applesauce used should not be hot and should be soft enough to be swallowed without chewing. The granules should not be chewed or crushed. If the granules/applesauce mixture is not used in its entirety, the remaining mixture should be discarded immediately.

For patients who have a nasogastric tube in place, esomeprazole magnesium delayed-release capsules can be opened and the intact granules emptied into a 60 mL catheter tipped syringe and mixed with 50 mL of water. It is important to only use a catheter tipped syringe when administering esomeprazole magnesium through a nasogastric tube. Replace the plunger and shake the syringe vigorously for 15 seconds. Hold the syringe with the tip up and check for granules remaining in the tip. Attach the syringe to a nasogastric tube and deliver the contents of the syringe through the nasogastric tube into the stomach. After administering the granules, the nasogastric tube should be flushed with additional water. Do not administer the granules if they have dissolved or disintegrated.

The mixture must be used immediately after preparation.

3 DOSAGE FORMS AND STRENGTHS

Esomeprazole magnesium delayed-release capsules, 20 mg - opaque, hard gelatin, powder blue colored capsules with “0382” and “20 mg” in black on the body.

Esomeprazole magnesium delayed-release capsules, 40 mg - opaque, hard gelatin, powder blue colored capsules with “0384” and “40 mg” in black on the body.

4 CONTRAINDICATIONS

Esomeprazole magnesium delayed-release capsules are contraindicated in patients with known hypersensitivity to substituted benzimidazoles or to any component of the formulation. Hypersensitivity reactions may include anaphylaxis, anaphylactic shock, angioedema, bronchospasm, acute tubulointerstitial nephritis, and urticaria [see Warnings and Precautions (5.2), Adverse Reactions (6)].

For information about contraindications of antibacterial agents (clarithromycin and amoxicillin) indicated in combination with esomeprazole magnesium delayed-release capsules, refer to the CONTRAINDICATIONS section of their package inserts.

5 WARNINGS AND PRECAUTIONS

5.1 Presence of Gastric Malignancy

In adults, symptomatic response to therapy with esomeprazole magnesium delayed-release capsules does not preclude the presence of gastric malignancy. Consider additional follow-up and diagnostic testing in adult patients who have a suboptimal response or an early symptomatic relapse after completing treatment with a PPI. In older patients, also consider an endoscopy.

5.2 Acute Tubulointerstitial Nephritis

Acute tubulointerstitial (TIN) nephritis has been observed in patients taking PPIs and may occur at any point during PPI therapy. Patients may present with varying signs and symptoms from symptomatic hypersensitivity reactions to non-specific symptoms of decreased renal function (e.g., malaise, nausea, anorexia). In reported case series, some patients were diagnosed on biopsy and in the absence of extra-renal manifestations (e.g., fever, rash or arthralgia). Discontinue esomeprazole magnesium delayed-release capsules and evaluate patients with suspected acute TIN [see Contraindications (4)].

5.3 Clostridium difficile-Associated Diarrhea

Published observational studies suggest that PPI therapy like esomeprazole magnesium delayed-release capsules may be associated with an increased risk of Clostridium difficile-associated diarrhea, especially in hospitalized patients. This diagnosis should be considered for diarrhea that does not improve [see Adverse Reactions (6.2)].

Patients should use the lowest dose and shortest duration of PPI therapy appropriate to the condition being treated.

Clostridium difficile-associated diarrhea (CDAD) has been reported with use of nearly all antibacterial agents. For more information specific to antibacterial agents (clarithromycin and amoxicillin) indicated for use in combination with esomeprazole magnesium delayed-release capsules, refer to Warnings and Precautions section of the corresponding prescribing information.

5.4 Bone Fracture

Several published observational studies suggest that proton pump inhibitor (PPI) therapy may be associated with an increased risk for osteoporosis-related fractures of the hip, wrist, or spine. The risk of fracture was increased in patients who received high-dose, defined as multiple daily doses, and long-term PPI therapy (a year or longer). Patients should use the lowest dose and shortest duration of PPI therapy appropriate to the condition being treated. Patients at risk for osteoporosis-related fractures should be managed according to established treatment guidelines [see Dosage and Administration (2) and Adverse Reactions (6.2)].

5.5 Cutaneous and Systemic Lupus Erythematosus

Cutaneous lupus erythematosus (CLE) and systemic lupus erythematosus (SLE) have been reported in patients taking PPIs, including esomeprazole. These events have occurred as both new onset and an exacerbation of existing autoimmune disease. The majority of PPI-induced lupus erythematosus cases were CLE.

The most common form of CLE reported in patients treated with PPIs was subacute CLE (SCLE) and occurred within weeks to years after continuous drug therapy in patients ranging from infants to the elderly. Generally, histological findings were observed without organ involvement.

Systemic lupus erythematosus (SLE) is less commonly reported than CLE in patients receiving PPIs. PPI associated SLE is usually milder than non-drug induced SLE. Onset of SLE typically occurred within days to years after initiating treatment primarily in patients ranging from young adults to the elderly. The majority of patients presented with rash; however, arthralgia and cytopenia were also reported.

Avoid administration of PPIs for longer than medically indicated. If signs or symptoms consistent with CLE or SLE are noted in patients receiving esomeprazole magnesium delayed-release capsules, discontinue the drug and refer the patient to the appropriate specialist for evaluation. Most patients improve with discontinuation of the PPI alone in 4 to 12 weeks. Serological testing (e.g., ANA) may be positive and elevated serological test results may take longer to resolve than clinical manifestations.

5.6 Interaction with Clopidogrel

Avoid concomitant use of esomeprazole magnesium delayed-release capsules with clopidogrel. Clopidogrel is a prodrug. Inhibition of platelet aggregation by clopidogrel is entirely due to an active metabolite. The metabolism of clopidogrel to its active metabolite can be impaired by use with concomitant medications, such as esomeprazole, that inhibit CYP2C19 activity. Concomitant use of clopidogrel with 40 mg esomeprazole reduces the pharmacological activity of clopidogrel. When using esomeprazole magnesium delayed-release capsules consider alternative anti-platelet therapy [see Drug Interactions (7.3) and Clinical Pharmacology (12.3)].

5.7 Cyanocobalamin (Vitamin B-12) Deficiency

Daily treatment with any acid-suppressing medications over a long period of time (e.g., longer than 3 years) may lead to malabsorption of cyanocobalamin (vitamin B-12) caused by hypo- or achlorhydria. Rare reports of cyanocobalamin deficiency occurring with acid-suppressing therapy have been reported in the literature. This diagnosis should be considered if clinical symptoms consistent with cyanocobalamin deficiency are observed.

5.8 Hypomagnesemia

Hypomagnesemia, symptomatic and asymptomatic, has been reported rarely in patients treated with PPIs for at least three months, in most cases after a year of therapy. Serious adverse events include tetany, arrhythmias, and seizures. In most patients, treatment of hypomagnesemia required magnesium replacement and discontinuation of the PPI.

For patients expected to be on prolonged treatment or who take PPIs with medications such as digoxin or drugs that may cause hypomagnesemia (e.g., diuretics), health care professionals may consider monitoring magnesium levels prior to initiation of PPI treatment and periodically [see Adverse Reactions (6.2)].

5.9 Interaction with St. John’s Wort or Rifampin

Drugs which induce CYP2C19 or CYP3A4 (such as St. John’s Wort or rifampin) can substantially decrease esomeprazole concentrations [see Drug Interactions (7.3)]. Avoid concomitant use of esomeprazole magnesium delayed-release capsules with St. John’s Wort or rifampin.

5.10 Interactions with Diagnostic Investigations for Neuroendocrine Tumors

Serum chromogranin A (CgA) levels increase secondary to drug-induced decreases in gastric acidity. The increased CgA level may cause false positive results in diagnostic investigations for neuroendocrine tumors. Healthcare providers should temporarily stop esomeprazole treatment at least 14 days before assessing CgA levels and consider repeating the test if initial CgA levels are high. If serial tests are performed (e.g., for monitoring), the same commercial laboratory should be used for testing, as reference ranges between tests may vary [see Clinical Pharmacology (12.2)].

5.11 Interaction with Methotrexate

Literature suggests that concomitant use of PPIs with methotrexate (primarily at high dose; see methotrexate prescribing information) may elevate and prolong serum levels of methotrexate and/or its metabolite, possibly leading to methotrexate toxicities. In high-dose methotrexate administration a temporary withdrawal of the PPI may be considered in some patients [see Drug Interactions (7.7)].

5.12 Fundic Gland Polyps

PPI use is associated with an increased risk of fundic gland polyps that increases with long-term use, especially beyond one year. Most PPI users who developed fundic gland polyps were asymptomatic and fundic gland polyps were identified incidentally on endoscopy. Use the shortest duration of PPI therapy appropriate to the condition being treated.

6 ADVERSE REACTIONS

The following serious adverse reactions are described below and elsewhere in labeling:

- Acute Tubulointerstitial Nephritis [see Warnings and Precautions (5.2)]
- Clostridium difficile-Associated Diarrhea [see Warnings and Precautions (5.3)]
- Bone Fracture [see Warnings and Precautions (5.4)]
- Cutaneous and Systemic Lupus Erythematosus [see Warnings and Precautions (5.5)]
- Cyanocobalamin (Vitamin B-12) Deficiency [see Warnings and Precautions (5.7)]
- Hypomagnesemia [see Warnings and Precautions (5.8)]
- Fundic Gland Polyps [see Warnings and Precautions (5.12)]

6.1 Clinical Trials Experience

Because clinical trials are conducted under widely varying conditions, adverse reaction rates observed in the clinical trials of a drug cannot be directly compared to rates in the clinical trials of another drug and may not reflect the rates observed in practice.

Adults

The safety of esomeprazole magnesium was evaluated in over 15,000 patients (aged 18 to 84 years) in clinical trials worldwide including over 8,500 patients in the United States and over 6,500 patients in Europe and Canada. Over 2,900 patients were treated in long-term studies for up to 6-12 months. In general, esomeprazole magnesium was well tolerated in both short and long-term clinical trials.

The safety in the treatment of healing of erosive esophagitis was assessed in four randomized comparative clinical trials, which included 1,240 patients on esomeprazole magnesium 20 mg, 2,434 patients on esomeprazole magnesium 40 mg, and 3,008 patients on omeprazole 20 mg daily. The most frequently occurring adverse reactions (≥1%) in all three groups were headache (5.5, 5, and 3.8, respectively) and diarrhea (no difference among the three groups). Nausea, flatulence, abdominal pain, constipation, and dry mouth occurred at similar rates among patients taking esomeprazole magnesium or omeprazole.

Additional adverse reactions that were reported as possibly or probably related to esomeprazole magnesium with an incidence <1% are listed below by body system:

Body as a Whole: abdomen enlarged, allergic reaction, asthenia, back pain, chest pain, substernal chest pain, facial edema, peripheral edema, hot flushes, fatigue, fever, flu-like disorder, generalized edema, leg edema, malaise, pain, rigors;

Cardiovascular: flushing, hypertension, tachycardia;

Endocrine: goiter;

Gastrointestinal: bowel irregularity, constipation aggravated, dyspepsia, dysphagia, dysplasia GI, epigastric pain, eructation, esophageal disorder, frequent stools, gastroenteritis, GI hemorrhage, GI symptoms not otherwise specified, hiccup, melena, mouth disorder, pharynx disorder, rectal disorder, serum gastrin increased, tongue disorder, tongue edema, ulcerative stomatitis, vomiting;

Hearing: earache, tinnitus;

Hematologic: anemia, anemia hypochromic, cervical lymphadenopathy, epistaxis, leukocytosis, leukopenia, thrombocytopenia;

Hepatic: bilirubinemia, hepatic function abnormal, SGOT increased, SGPT increased;

Metabolic/Nutritional: glycosuria, hyperuricemia, hyponatremia, increased alkaline phosphatase, thirst, vitamin B12 deficiency, weight increase, weight decrease;

Musculoskeletal: arthralgia, arthritis aggravated, arthropathy, cramps, fibromyalgia syndrome, hernia, polymyalgia rheumatica;

Nervous System/Psychiatric: anorexia, apathy, appetite increased, confusion, depression aggravated, dizziness, hypertonia, nervousness, hypoesthesia, impotence, insomnia, migraine, migraine aggravated, paresthesia, sleep disorder, somnolence, tremor, vertigo, visual field defect;

Reproductive: dysmenorrhea, menstrual disorder, vaginitis;

Respiratory: asthma aggravated, coughing, dyspnea, larynx edema, pharyngitis, rhinitis, sinusitis;

Skin and Appendages: acne, angioedema, dermatitis, pruritus, pruritus ani, rash, rash erythematous, rash maculo-papular, skin inflammation, sweating increased, urticaria;

Special Senses: otitis media, parosmia, taste loss, taste perversion;

Urogenital: abnormal urine, albuminuria, cystitis, dysuria, fungal infection, hematuria, micturition frequency, moniliasis, genital moniliasis, polyuria;

Visual: conjunctivitis, vision abnormal.

The following potentially clinically significant laboratory changes in clinical trials, irrespective of relationship to esomeprazole magnesium, were reported in ≤1% of patients: increased creatinine, uric acid, total bilirubin, alkaline phosphatase, ALT, AST, hemoglobin, white blood cell count, platelets, serum gastrin, potassium, sodium, thyroxine and thyroid stimulating hormone [see Clinical Pharmacology (12)]. Decreases were seen in hemoglobin, white blood cell count, platelets, potassium, sodium, and thyroxine.

Endoscopic findings that were reported as adverse reactions include: duodenitis, esophagitis, esophageal stricture, esophageal ulceration, esophageal varices, gastric ulcer, gastritis, hernia, benign polyps or nodules, Barrett’s esophagus, and mucosal discoloration.

The incidence of treatment-related adverse reactions during 6-month maintenance treatment was similar to placebo. There were no differences in types of related adverse reactions seen during maintenance treatment up to 12 months compared to short-term treatment.

Two placebo-controlled studies were conducted in 710 patients for the treatment of symptomatic gastroesophageal reflux disease. The most common adverse reactions that were reported as possibly or probably related to esomeprazole magnesium were diarrhea (4.3%), headache (3.8%), and abdominal pain (3.8%).

Pediatrics

The safety of esomeprazole magnesium was evaluated in 316 pediatric and adolescent patients aged 1 to 17 years in four clinical trials for the treatment of symptomatic GERD [see Clinical Studies (14.2)]. In 109 pediatric patients aged 1 to 11 years, the most frequently reported (at least 1%) treatment-related adverse reactions in these patients were diarrhea (2.8%), headache (1.9%) and somnolence (1.9%). In 149 pediatric patients aged 12 to 17 years the most frequently reported (at least 2%) treatment-related adverse reactions in these patients were headache (8.1%), abdominal pain (2.7%), diarrhea (2%), and nausea (2%).

The safety of esomeprazole magnesium was evaluated in 167 pediatric patients from birth to <1 year of age in three clinical trials [see Clinical Studies (14.3)]. In a study that included 26 pediatric patients aged birth to 1 month there were no treatment related adverse reactions. In a study that included 43 pediatric patients age 1 to 11 months, inclusive the most frequently reported (at least 5%) adverse reactions, irrespective of causality, were irritability and vomiting. In a study that included 98 pediatric patients, age 1 to 11 months, inclusive exposed to esomeprazole for up to 6 weeks (including 39 patients randomized to the withdrawal phase), there were 4 treatment-related adverse reactions: abdominal pain (1%), regurgitation (1%), tachypnea (1%), and increased ALT (1%).

No new safety concerns were identified in pediatric patients.

Combination Treatment with Amoxicillin and Clarithromycin

In clinical trials using combination therapy with esomeprazole magnesium plus amoxicillin and clarithromycin, no additional adverse reactions specific to these drug combinations were observed. Adverse reactions that occurred were limited to those observed when using esomeprazole magnesium, amoxicillin, or clarithromycin alone.

The most frequently reported drug-related adverse reactions for patients who received triple therapy for 10 days were diarrhea (9.2%), taste perversion (6.6%), and abdominal pain (3.7%). No treatment-emergent adverse reactions were observed at higher rates with triple therapy than were observed with esomeprazole magnesium alone.

For more information on adverse reactions with amoxicillin or clarithromycin, refer to their package inserts, Adverse Reactions sections.

In clinical trials using combination therapy with esomeprazole magnesium plus amoxicillin and clarithromycin, no additional increased laboratory abnormalities particular to these drug combinations were observed.

For more information on laboratory changes with amoxicillin or clarithromycin, refer to their package inserts, Adverse Reactions section.

6.2 Postmarketing Experience

The following adverse reactions have been identified during post-approval use of esomeprazole magnesium. Because these reactions are reported voluntarily from a population of uncertain size, it is not always possible to reliably estimate their frequency or establish a causal relationship to drug exposure. These reports are listed below by body system:

Blood and Lymphatic: agranulocytosis, pancytopenia;

Eye: blurred vision;

Gastrointestinal: pancreatitis; stomatitis; microscopic colitis; fundic gland polyps;

Hepatobiliary: hepatic failure, hepatitis with or without jaundice;

Immune System: anaphylactic reaction/shock; systemic lupus erythematosus;

Infections and Infestations: GI candidiasis; Clostridium difficile-associated diarrhea;

Metabolism and nutritional disorders: hypomagnesemia, with or without hypocalcemia and/or hypokalemia;

Musculoskeletal and Connective Tissue: muscular weakness, myalgia, bone fracture;

Nervous System: hepatic encephalopathy, taste disturbance;

Psychiatric: aggression, agitation, depression, hallucination;

Renal and Urinary: interstitial nephritis;

Reproductive System and Breast: gynecomastia;

Respiratory, Thoracic, and Mediastinal: bronchospasm;

Skin and Subcutaneous Tissue: alopecia, erythema multiforme, hyperhidrosis, photosensitivity, Stevens-Johnson syndrome, toxic epidermal necrolysis (some fatal), cutaneous lupus erythematosus.

7 DRUG INTERACTIONS

7.1 Interference with Antiretroviral Therapy

Concomitant use of atazanavir and nelfinavir with proton pump inhibitors is not recommended. Co-administration of atazanavir with proton pump inhibitors is expected to substantially decrease atazanavir plasma concentrations and may result in a loss of therapeutic effect and the development of drug resistance. Co-administration of saquinavir with proton pump inhibitors is expected to increase saquinavir concentrations, which may increase toxicity and require dose reduction.

Omeprazole, of which esomeprazole is an enantiomer, has been reported to interact with some antiretroviral drugs. The clinical importance and the mechanisms behind these interactions are not always known. Increased gastric pH during omeprazole treatment may change the absorption of the antiretroviral drug. Other possible interaction mechanisms are via CYP2C19.

Reduced concentrations of atazanavir and nelfinavir

For some antiretroviral drugs, such as atazanavir and nelfinavir, decreased serum levels have been reported when given together with omeprazole. Following multiple doses of nelfinavir (1250 mg, twice daily) and omeprazole (40 mg daily), AUC was decreased by 36% and 92%, Cmax by 37% and 89% and Cmin by 39% and 75% respectively for nelfinavir and M8. Following multiple doses of atazanavir (400 mg, daily) and omeprazole (40 mg, daily, 2 hours before atazanavir), AUC was decreased by 94%, Cmax by 96%, and Cmin by 95%. Concomitant administration with omeprazole and drugs such as atazanavir and nelfinavir is therefore not recommended.

Increased concentrations of saquinavir

For other antiretroviral drugs, such as saquinavir, elevated serum levels have been reported, with an increase in AUC by 82%, in Cmax by 75%, and in Cmin by 106%, following multiple dosing of saquinavir/ritonavir (1000/100 mg) twice daily for 15 days with omeprazole 40 mg daily co-administered days 11 to 15. Therefore, clinical and laboratory monitoring for saquinavir toxicity is recommended during concurrent use with esomeprazole magnesium delayed-release capsules. Dose reduction of saquinavir should be considered from the safety perspective for individual patients.

There are also some antiretroviral drugs of which unchanged serum levels have been reported when given with omeprazole.

7.2 Drugs for Which Gastric pH Can Affect Bioavailability

Due to its effects on gastric acid secretion, esomeprazole can reduce the absorption of drugs where gastric pH is an important determinant of their bioavailability. Like with other drugs that decrease the intragastric acidity, the absorption of drugs such as ketoconazole, atazanavir, iron salts, erlotinib, and mycophenolate mofetil (MMF) can decrease, while the absorption of drugs such as digoxin can increase during treatment with esomeprazole. Esomeprazole is an enantiomer of omeprazole. Concomitant treatment with omeprazole (20 mg daily) and digoxin in healthy subjects increased the bioavailability of digoxin by 10% (30% in two subjects). Co-administration of digoxin with esomeprazole magnesium delayed-release capsules is expected to increase the systemic exposure of digoxin. Therefore, patients may need to be monitored when digoxin is taken concomitantly with esomeprazole magnesium delayed-release capsules.

Co-administration of omeprazole in healthy subjects and in transplant patients receiving MMF has been reported to reduce the exposure to the active metabolite, mycophenolic acid (MPA), possibly due to a decrease in MMF solubility at an increased gastric pH. The clinical relevance of reduced MPA exposure on organ rejection has not been established in transplant patients receiving esomeprazole magnesium and MMF. Use esomeprazole magnesium delayed-release capsules with caution in transplant patients receiving MMF [see Clinical Pharmacology (12.3)].

7.3 Effects on Hepatic Metabolism/Cytochrome P-450 Pathways

Esomeprazole is extensively metabolized in the liver by CYP2C19 and CYP3A4. In vitro and in vivo studies have shown that esomeprazole is not likely to inhibit CYPs 1A2, 2A6, 2C9, 2D6, 2E1, and 3A4. No clinically relevant interactions with drugs metabolized by these CYP enzymes would be expected. Drug interaction studies have shown that esomeprazole does not have any clinically significant interactions with phenytoin, warfarin, quinidine, clarithromycin, or amoxicillin.

However, postmarketing reports of changes in prothrombin measures have been received among patients on concomitant warfarin and esomeprazole therapy. Increases in INR and prothrombin time may lead to abnormal bleeding and even death. Patients treated with proton pump inhibitors and warfarin concomitantly may need to be monitored for increases in INR and prothrombin time.

Esomeprazole may potentially interfere with CYP2C19, the major esomeprazole metabolizing enzyme. Co-administration of esomeprazole 30 mg and diazepam, a CYP2C19 substrate, resulted in a 45% decrease in clearance of diazepam.

Clopidogrel

Clopidogrel is metabolized to its active metabolite in part by CYP2C19. Concomitant use of esomeprazole 40 mg results in reduced plasma concentrations of the active metabolite of clopidogrel and a reduction in platelet inhibition. Avoid concomitant administration of esomeprazole magnesium delayed-release capsules with clopidogrel. When using esomeprazole magnesium delayed-release capsules, consider use of alternative anti-platelet therapy [see Clinical Pharmacology (12.3)].

Omeprazole acts as an inhibitor of CYP2C19. Omeprazole, given in doses of 40 mg daily for one week to 20 healthy subjects in cross-over study, increased Cmax and AUC of cilostazol by 18% and 26% respectively. Cmax and AUC of one of its active metabolites, 3,4-dihydrocilostazol, which has 4-7 times the activity of cilostazol, were increased by 29% and 69%, respectively. Co-administration of cilostazol with esomeprazole is expected to increase concentrations of cilostazol and its above mentioned active metabolite. Therefore, a dose reduction of cilostazol from 100 mg twice daily to 50 mg twice daily should be considered.

Concomitant administration of esomeprazole and a combined inhibitor of CYP2C19 and CYP3A4, such as voriconazole, may result in more than doubling of the esomeprazole exposure. Dose adjustment of esomeprazole is not normally required. However, in patients with Zollinger-Ellison’s Syndrome, who may require higher doses up to 240 mg/day, dose adjustment may be considered.

Drugs known to induce CYP2C19 or CYP3A4 or both (such as rifampin) may lead to decreased esomeprazole serum levels. Omeprazole, of which esomeprazole is an enantiomer, has been reported to interact with St. John’s Wort, an inducer of CYP3A4. In a cross-over study in 12 healthy male subjects, St. John’s Wort (300 mg three times daily for 14 days) significantly decreased the systemic exposure of omeprazole in CYP2C19 poor metabolisers (Cmax and AUC decreased by 37.5% and 37.9%, respectively) and extensive metabolisers (Cmax and AUC decreased by 49.6 % and 43.9%, respectively). Avoid concomitant use of St. John’s Wort or rifampin with esomeprazole magnesium delayed-release capsules.

7.4 Interactions with Investigations of Neuroendocrine Tumors

Drug-induced decrease in gastric acidity results in enterochromaffin-like cell hyperplasia and increased Chromogranin A levels which may interfere with investigations for neuroendocrine tumors [see Warnings and Precautions (5.10) and Clinical Pharmacology (12.2)].

7.5 Tacrolimus

Concomitant administration of esomeprazole and tacrolimus may increase the serum levels of tacrolimus.

7.6 Combination Therapy with Clarithromycin

Co-administration of esomeprazole, clarithromycin, and amoxicillin has resulted in increases in the plasma levels of esomeprazole and 14-hydroxyclarithromycin [see Clinical Pharmacology (12.4)].

Concomitant administration of clarithromycin with other drugs can lead to serious adverse reactions due to drug interactions [see Warnings and Precautions in prescribing information for clarithromycin]. Because of these drug interactions, clarithromycin is contraindicated for co-administration with certain drugs [see Contraindications in prescribing information for clarithromycin].

7.7 Methotrexate

Case reports, published population pharmacokinetic studies, and retrospective analyses suggest that concomitant administration of PPIs and methotrexate (primarily at high dose; see methotrexate prescribing information) may elevate and prolong serum levels of methotrexate and/or its metabolite hydroxymethotrexate. However, no formal drug interaction studies of methotrexate with PPIs have been conducted [see Warnings and Precautions (5.11)].

8 USE IN SPECIFIC POPULATIONS

8.1 Pregnancy

Risk Summary

There are no adequate and well-controlled studies with esomeprazole magnesium in pregnant women. Esomeprazole is the S-isomer of omeprazole. Available epidemiologic data fail to demonstrate an increased risk of major congenital malformations or other adverse pregnancy outcomes with first trimester omeprazole use. Reproduction studies in rats and rabbits resulted in dose-dependent embryo-lethality at omeprazole doses that were approximately 3.4 to 34 times an oral human dose of 40 mg (based on a body surface area for a 60 kg person).

Teratogenicity was not observed in animal reproduction studies with administration of oral esomeprazole magnesium in rats and rabbits with doses about 68 times and 42 times, respectively, an oral human dose of 40 mg (based on a body surface area basis for a 60 kg person). Changes in bone morphology were observed in offspring of rats dosed through most of pregnancy and lactation at doses equal to or greater than approximately 34 times an oral human dose of 40 mg. When maternal administration was confined to gestation only, there were no effects on bone physeal morphology in the offspring at any age [see Data].

The estimated background risks of major birth defects and miscarriage for the indicated population are unknown. All pregnancies have a background risk of birth defect, loss or other adverse outcomes. In the U.S. general population, the estimated background risk of major birth defects and miscarriage in clinically recognized pregnancies is 2% to 4% and 15% to 20%, respectively.

Data

Human Data

Esomeprazole is the S-isomer of omeprazole. Four epidemiological studies compared the frequency of congenital abnormalities among infants born to women who used omeprazole during pregnancy with the frequency of abnormalities among infants of women exposed to H2-receptor antagonists or other controls.

A population-based retrospective cohort epidemiological study from the Swedish Medical Birth Registry, covering approximately 99% of pregnancies, from 1995 to 1999, reported on 955 infants (824 exposed during the first trimester with 39 of these exposed beyond first trimester, and 131 exposed after the first trimester) whose mothers used omeprazole during pregnancy. The number of infants exposed in utero to omeprazole that had any malformation, low birth weight, low Apgar score, or hospitalization was similar to the number observed in this population. The number of infants born with ventricular septal defects and the number of stillborn infants was slightly higher in the omeprazole-exposed infants than the expected number in this population.

A population-based retrospective cohort study covering all live births in Denmark from 1996 to 2009, reported on 1,800 live births whose mothers used omeprazole during the first trimester of pregnancy and 837,317 live births whose mothers did not use any proton pump inhibitor. The overall rate of birth defects in infants born to mothers with first trimester exposure to omeprazole was 2.9% and 2.6% in infants born to mothers not exposed to any proton pump inhibitor during the first trimester.

A retrospective cohort study reported on 689 pregnant women exposed to either H2-blockers or omeprazole in the first trimester (134 exposed to omeprazole) and 1,572 pregnant women unexposed to either during the first trimester. The overall malformation rate in offspring born to mothers with first trimester exposure to omeprazole, an H2-blocker, or were unexposed was 3.6%, 5.5%, and 4.1% respectively.

A small prospective observational cohort study followed 113 women exposed to omeprazole during pregnancy (89% with first trimester exposures). The reported rate of major congenital malformations was 4% in the omeprazole group, 2% in controls exposed to non-teratogens, and 2.8% in disease paired controls. Rates of spontaneous and elective abortions, preterm deliveries, gestational age at delivery, and mean birth weight were similar among the groups.

Several studies have reported no apparent adverse short-term effects on the infant when single dose oral or intravenous omeprazole was administered to over 200 pregnant women as premedication for cesarean section under general anesthesia.

Animal Data

Omeprazole

Reproductive studies conducted with omeprazole in rats at oral doses up to 138 mg/kg/day (about 34 times an oral human dose of 40 mg on a body surface area basis) and in rabbits at doses up to 69.1 mg/kg/day (about 34 times an oral human dose of 40 mg on a body surface area basis) during organogenesis did not disclose any evidence for a teratogenic potential of omeprazole. In rabbits, omeprazole in a dose range of 6.9 to 69.1 mg/kg/day (about 3.4 to 34 times an oral human dose of 40 mg on a body surface area basis) administered during organogenesis produced dose-related increases in embryo-lethality, fetal resorptions, and pregnancy disruptions. In rats, dose-related embryo/fetal toxicity and postnatal developmental toxicity were observed in offspring resulting from parents treated with omeprazole at 13.8 to 138.0 mg/kg/day (about 3.4 to 34 times an oral human dose of 40 mg on a body surface area basis), administered prior to mating through the lactation period.

Esomeprazole

No effects on embryo-fetal development were observed in reproduction studies with esomeprazole magnesium in rats at oral doses up to 280 mg/kg/day (about 68 times an oral human dose of 40 mg on a body surface area basis) or in rabbits at oral doses up to 86 mg/kg/day (about 41 times an oral human dose of 40 mg on a body surface area basis) administered during organogenesis.

A pre- and postnatal developmental toxicity study in rats with additional endpoints to evaluate bone development was performed with esomeprazole magnesium at oral doses of 14 to 280 mg/kg/day (about 3.4 to 68 times an oral human dose of 40 mg on a body surface area basis). Neonatal/early postnatal (birth to weaning) survival was decreased at doses equal to or greater than 138 mg/kg/day (about 34 times an oral human dose of 40 mg on a body surface area basis). Body weight and body weight gain were reduced and neurobehavioral or general developmental delays in the immediate post-weaning timeframe were evident at doses equal to or greater than 69 mg/kg/day (about 17 times an oral human dose of 40 mg on a body surface area basis). In addition, decreased femur length, width and thickness of cortical bone, decreased thickness of the tibial growth plate and minimal to mild bone marrow hypocellularity were noted at doses equal to or greater than 14 mg/kg/day (about 3.4 times an oral human dose of 40 mg on a body surface area basis). Physeal dysplasia in the femur was observed in offspring of rats treated with oral doses of esomeprazole magnesium at doses equal to or greater than 138 mg/kg/day (about 34 times an oral human dose of 40 mg on a body surface area basis).

Effects on maternal bone were observed in pregnant and lactating rats in a pre- and postnatal toxicity study when esomeprazole magnesium was administered at oral doses of 14 to 280 mg/kg/day (about 3.4 to 68 times an oral human dose of 40 mg on a body surface area basis). When rats were dosed from gestational day 7 through weaning on postnatal day 21, a statistically significant decrease in maternal femur weight of up to 14% (as compared to placebo treatment) was observed at doses equal to or greater than 138 mg/kg/day (about 34 times an oral human dose of 40 mg on a body surface area basis).

A pre- and postnatal development study in rats with esomeprazole strontium (using equimolar doses compared to esomeprazole magnesium study) produced similar results in dams and pups as described above.

A follow-up developmental toxicity study in rats with further time points to evaluate pup bone development from postnatal day 2 to adulthood was performed with esomeprazole magnesium at oral doses of 280 mg/kg/day (about 68 times an oral human dose of 40 mg on a body surface area basis) where esomeprazole administration was from either gestational day 7 or gestational day 16 until parturition. When maternal administration was confined to gestation only, there were no effects on bone physeal morphology in the offspring at any age.

8.2 Lactation

Risk Summary

Esomeprazole is the S-isomer of omeprazole and limited data suggest that omeprazole may be present in human milk. There are no clinical data on the effects of esomeprazole on the breastfed infant or on milk production. The developmental and health benefits of breastfeeding should be considered along with the mother’s clinical need for esomeprazole magnesium delayed-release capsules and any potential adverse effects on the breastfed infant from esomeprazole magnesium or from the underlying maternal condition.

8.4 Pediatric Use

The safety and effectiveness of esomeprazole magnesium have been established in pediatric patients 1 to 17 years of age for short-term treatment (up to eight weeks) of GERD. The safety and effectiveness of esomeprazole magnesium have been established in pediatric patients 1 month to less than 1 year for short-term treatment (up to 6 weeks) of erosive esophagitis due to acid-mediated GERD. However, the safety and effectiveness of esomeprazole magnesium have not been established in patients less than 1 month of age.

1 to 17 years of age

Use of esomeprazole magnesium in pediatric and adolescent patients 1 to 17 years of age for short-term treatment (up to eight weeks) of GERD is supported by extrapolation of results from adequate and well-controlled studies for adults and safety and pharmacokinetic studies performed in pediatric and adolescent patients [see Dosage and Administration (2), Adverse Reactions (6.1), Clinical Pharmacology (12.3), and Clinical Studies (14.3)]. The safety and effectiveness of esomeprazole magnesium for other pediatric uses have not been established.

Erosive esophagitis due to acid-mediated GERD in infants 1 month to less than one year of age

Use of esomeprazole magnesium in pediatric patients 1 month to less than 1 year of age for treatment (up to 6 weeks) of erosive esophagitis due to acid-mediated GERD is supported by extrapolation of results from adequate and well-controlled studies for adults and safety, pharmacokinetic, and pharmacodynamic studies performed in pediatric patients [see Dosage and Administration (2), Adverse Reactions (6.1), Clinical Pharmacology (12.3), and Clinical Studies (14.3)].

Symptomatic GERD in infants 1 month to less than one year of age

There was no statistically significant difference between esomeprazole magnesium and placebo in the rate of discontinuation due to symptom worsening in a multicenter, randomized, double-blind, controlled, treatment-withdrawal study of 98 patients ages 1 to 11 months, inclusive. Patients were enrolled if they had either a clinical diagnosis of suspected GERD, symptomatic GERD, or endoscopically proven GERD. Twenty of 98 enrolled patients underwent endoscopy, and 6 patients were found to have erosive esophagitis on endoscopy at baseline. All patients received esomeprazole magnesium delayed-release oral suspension once daily during a two-week, open-label phase of the study.

There were 80 patients who attained a pre-specified level of symptom improvement and who entered the double-blind phase, in which they were randomized in equal proportions to receive esomeprazole magnesium or placebo for the next four weeks. Efficacy was assessed by observing the time from randomization to study discontinuation due to symptom worsening during the four-week, treatment-withdrawal phase.

The following pharmacokinetic and pharmacodynamic information was obtained in pediatric patients with GERD aged birth to less than one year of age. In infants (1 to 11 months old, inclusive) given esomeprazole magnesium 1 mg/kg once daily, the percent time with intragastric pH > 4 increased from 29% at baseline to 69% on Day 7, which is similar to the pharmacodynamic effect in adults [see Clinical Pharmacology (12.2)]. Apparent clearance (CL/F) increases with age in pediatric patients from birth to 2 years of age.

Neonates 0 to 1 month of age

Following administration of oral esomeprazole magnesium in neonates the geometric mean (range) for the apparent clearance (CL/F) was 0.55 L/h/kg (0.25-1.6 L/h/kg).

The safety and effectiveness of esomeprazole magnesium in neonates have not been established.

Juvenile Animal Data

In a juvenile rat toxicity study, esomeprazole was administered with both magnesium and strontium salts at oral doses about 34 to 68 times a daily human dose of 40 mg based on body surface area. Increases in death were seen at the high dose, and at all doses of esomeprazole, there were decreases in body weight, body weight gain, femur weight and femur length, and decreases in overall growth [see Nonclinical Toxicology (13.2)].

8.5 Geriatric Use

Of the total number of patients who received esomeprazole magnesium in clinical trials, 1459 were 65 to 74 years of age and 354 patients were ≥ 75 years of age.

No overall differences in safety and efficacy were observed between the elderly and younger individuals, and other reported clinical experience has not identified differences in responses between the elderly and younger patients, but greater sensitivity of some older individuals cannot be ruled out.

10 OVERDOSAGE

A single oral dose of esomeprazole at 510 mg/kg (about 124 times the human dose on a body surface area basis), was lethal to rats. The major signs of acute toxicity were reduced motor activity, changes in respiratory frequency, tremor, ataxia, and intermittent clonic convulsions.

The symptoms described in connection with deliberate esomeprazole magnesium overdose (limited experience of doses in excess of 240 mg/day) are transient. Single doses of 80 mg of esomeprazole were uneventful. Reports of overdosage with omeprazole in humans may also be relevant. Doses ranged up to 2,400 mg (120 times the usual recommended clinical dose). Manifestations were variable, but included confusion, drowsiness, blurred vision, tachycardia, nausea, diaphoresis, flushing, headache, dry mouth, and other adverse reactions similar to those seen in normal clinical experience (see omeprazole package insert - Adverse Reactions). No specific antidote for esomeprazole is known. Since esomeprazole is extensively protein bound, it is not expected to be removed by dialysis. In the event of overdosage, treatment should be symptomatic and supportive.

As with the management of any overdose, the possibility of multiple drug ingestion should be considered. For current information on treatment of any drug overdose contact a Poison Control Center at 1–800–222–1222.

11 DESCRIPTION

The active ingredient in the proton pump inhibitor esomeprazole magnesium delayed-release capsules for oral administration is bis(5-methoxy-2-[(S)-[(4-methoxy-3,5-dimethyl-2-pyridinyl)methyl]sulfinyl]-1H-benzimidazole-1-yl) magnesium trihydrate. Esomeprazole is the S-isomer of omeprazole, which is a mixture of the S- and R- isomers. (Initial U.S. approval of esomeprazole magnesium: 2001). Its molecular formula is (C17H18N3O3S)2Mg x 3 H2O with molecular weight of 767.2 as a trihydrate and 713.1 on an anhydrous basis. The structural formula is:

Figure 1

The magnesium salt is a white to slightly colored crystalline powder. It contains 3 moles of water of solvation and is slightly soluble in water. The stability of esomeprazole magnesium is a function of pH; it rapidly degrades in acidic media, but it has acceptable stability under alkaline conditions. At pH 6.8 (buffer), the half-life of the magnesium salt is about 19 hours at 25°C and about 8 hours at 37°C.

Esomeprazole magnesium is supplied in delayed-release capsules. Each delayed-release capsule contains 20 mg, or 40 mg of esomeprazole (present as 22.3 mg, or 44.5 mg esomeprazole magnesium trihydrate) in the form of enteric-coated granules with the following inactive ingredients: glyceryl monostearate 40-55, hydroxypropyl cellulose, hypromellose, magnesium stearate, methacrylic acid copolymer type C, polysorbate 80, sugar spheres, talc, and triethyl citrate. The capsule shells have the following inactive ingredients: gelatin, FD&C Blue #1, FD&C Red #40, D&C Red #28, titanium dioxide, shellac, ethyl alcohol, isopropyl alcohol, n-butyl alcohol, propylene glycol, sodium hydroxide, polyvinyl pyrrolidone, and TekPrint SW-9008 black ink.

12 CLINICAL PHARMACOLOGY

12.1 Mechanism of Action

Esomeprazole is a proton pump inhibitor that suppresses gastric acid secretion by specific inhibition of the H^+/K^+-ATPase in the gastric parietal cell. The S- and R-isomers of omeprazole are protonated and converted in the acidic compartment of the parietal cell forming the active inhibitor, the achiral sulphenamide. By acting specifically on the proton pump, esomeprazole blocks the final step in acid production, thus reducing gastric acidity. This effect is dose-related up to a daily dose of 20 to 40 mg and leads to inhibition of gastric acid secretion.

12.2 Pharmacodynamics

Antisecretory Activity

The effect of esomeprazole magnesium on intragastric pH was determined in patients with symptomatic gastroesophageal reflux disease in two separate studies. In the first study of 36 patients, esomeprazole magnesium 40 mg and 20 mg were administered over 5 days. The results are shown in the Table 3:

Table 3: Effect on Intragastric pH on Day 5 (N=36)
Parameter | Esomeprazole Magnesium; 40 mg | Esomeprazole Magnesium; 20 mg
% Time Gastric pH >4 [Gastric pH was measured over a 24-hour period] (Hours) | 70% [p< 0.01 esomeprazole magnesium 40 mg vs. esomeprazole magnesium 20 mg]; (16.8 h) | 53%; (12.7 h)
Coefficient of variation | 26% | 37%
Median 24 Hour pH | 4.9 | 4.1
Coefficient of variation | 16% | 27%

In a second study, the effect on intragastric pH of esomeprazole magnesium 40 mg administered once daily over a five day period was similar to the first study, (% time with pH > 4 was 68% or 16.3 hours).

Serum Gastrin Effects

The effect of esomeprazole magnesium on serum gastrin concentrations was evaluated in approximately 2,700 patients in clinical trials up to 8 weeks and in over 1,300 patients for up to 6 to 12 months. The mean fasting gastrin level increased in a dose-related manner. This increase reached a plateau within two to three months of therapy and returned to baseline levels within four weeks after discontinuation of therapy.

Increased gastrin causes enterochromaffin-like cell hyperplasia and increased serum Chromogranin A (CgA) levels. The increased CgA levels may cause false positive results in diagnostic investigations for neuroendocrine tumors. Healthcare providers should temporarily stop esomeprazole treatment at least 14 days before assessing CgA levels and consider repeating the test if initial CgA levels are high.

Enterochromaffin-like (ECL) Cell Effects

In 24-month carcinogenicity studies of omeprazole in rats, a dose-related significant occurrence of gastric ECL cell carcinoid tumors and ECL cell hyperplasia was observed in both male and female animals [see Nonclinical Toxicology (13.1)]. Carcinoid tumors have also been observed in rats subjected to fundectomy or long-term treatment with other proton pump inhibitors or high doses of H2-receptor antagonists.

Human gastric biopsy specimens have been obtained from more than 3,000 patients (both children and adults) treated with omeprazole in long-term clinical trials. The incidence of ECL cell hyperplasia in these studies increased with time; however, no case of ECL cell carcinoids, dysplasia, or neoplasia has been found in these patients.

In over 1,000 patients treated with esomeprazole magnesium (10, 20 or 40 mg/day) up to 6 to 12 months, the prevalence of ECL cell hyperplasia increased with time and dose. No patient developed ECL cell carcinoids, dysplasia, or neoplasia in the gastric mucosa.

Endocrine Effects

Esomeprazole magnesium had no effect on thyroid function when given in oral doses of 20 or 40 mg for 4 weeks. Other effects of esomeprazole magnesium on the endocrine system were assessed using omeprazole studies. Omeprazole given in oral doses of 30 or 40 mg for 2 to 4 weeks had no effect on carbohydrate metabolism, circulating levels of parathyroid hormone, cortisol, estradiol, testosterone, prolactin, cholecystokinin, or secretin.

12.3 Pharmacokinetics

Absorption

Esomeprazole magnesium delayed-release capsules and esomeprazole magnesium for delayed-release oral suspension contain a bioequivalent enteric-coated granule formulation of esomeprazole magnesium. Bioequivalency is based on a single dose (40 mg) study in 94 healthy male and female volunteers under fasting condition. After oral administration, peak plasma levels (Cmax) occur at approximately 1.5 hours (Tmax). The Cmax increases proportionally when the dose is increased, and there is a three-fold increase in the area under the plasma concentration-time curve (AUC) from 20 to 40 mg. At repeated once-daily dosing with 40 mg, the systemic bioavailability is approximately 90% compared to 64% after a single dose of 40 mg. The mean exposure (AUC) to esomeprazole increases from 4.32 µmol*hr/L on Day 1 to 11.2 µmol*hr/L on Day 5 after 40 mg once daily dosing.

The AUC after administration of a single 40 mg dose of esomeprazole magnesium is decreased by 43% to 53% after food intake compared to fasting conditions. Esomeprazole magnesium delayed-release capsules should be taken at least one hour before meals.

The pharmacokinetic profile of esomeprazole magnesium was determined in 36 patients with symptomatic gastroesophageal reflux disease following repeated once daily administration of 20 mg and 40 mg capsules of esomeprazole magnesium over a period of five days. The results are shown in the Table 4:

Table 4: Pharmacokinetic Parameters of Esomeprazole Magnesium on Day 5 Following Oral Dosing for 5 Days
Parameter [Values represent the geometric mean, except the Tmax, which is the arithmetic mean; CV = Coefficient of variation] (CV) | Esomeprazole Magnesium; 40 mg | Esomeprazole Magnesium; 20 mg
AUC (μmol·h/L) | 12.6 (42%) | 4.2 (59%)
Cmax (μmol/L) | 4.7 (37%) | 2.1 (45%)
Tmax (h) | 1.6 | 1.6
t1/2 (h) | 1.5 | 1.2

Distribution

Esomeprazole is 97% bound to plasma proteins. Plasma protein binding is constant over the concentration range of 2 to 20 μmol/L. The apparent volume of distribution at steady state in healthy volunteers is approximately 16 L.

Elimination

Metabolism

Esomeprazole is extensively metabolized in the liver by the cytochrome P450 (CYP) enzyme system. The metabolites of esomeprazole lack antisecretory activity. The major part of esomeprazole’s metabolism is dependent upon the CYP2C19 isoenzyme, which forms the hydroxy and desmethyl metabolites. The remaining amount is dependent on CYP3A4 which forms the sulphone metabolite. CYP2C19 isoenzyme exhibits polymorphism in the metabolism of esomeprazole, since some 3% of Caucasians and 15 to 20% of Asians lack CYP2C19 and are termed Poor Metabolizers. At steady state, the ratio of AUC in Poor Metabolizers to AUC in the rest of the population (Extensive Metabolizers) is approximately 2.

Following administration of equimolar doses, the S- and R-isomers are metabolized differently by the liver, resulting in higher plasma levels of the S- than of the R-isomer.

Excretion

The plasma elimination half-life of esomeprazole is approximately 1 to 1.5 hours. Less than 1% of parent drug is excreted in the urine. Approximately 80% of an oral dose of esomeprazole is excreted as inactive metabolites in the urine, and the remainder is found as inactive metabolites in the feces.

Combination Therapy with Antimicrobials

Esomeprazole magnesium 40 mg once daily was given in combination with clarithromycin 500 mg twice daily and amoxicillin 1000 mg twice daily for 7 days to 17 healthy male and female subjects. The mean steady state AUC and Cmax of esomeprazole increased by 70% and 18%, respectively during triple combination therapy compared to treatment with esomeprazole alone. The observed increase in esomeprazole exposure during co-administration with clarithromycin and amoxicillin is not expected to produce significant safety concerns.

The pharmacokinetic parameters for clarithromycin and amoxicillin were similar during triple combination therapy and administration of each drug alone. However, the mean AUC and Cmax for 14-hydroxyclarithromycin increased by 19% and 22%, respectively, during triple combination therapy compared to treatment with clarithromycin alone. This increase in exposure to 14-hydroxyclarithromycin is not considered to be clinically significant.

Concomitant Use with Clopidogrel

Results from a crossover study in healthy subjects have shown a pharmacokinetic interaction between clopidogrel (300 mg loading dose/75 mg daily maintenance dose) and esomeprazole (40 mg p.o. once daily) when co-administered for 30 days. Exposure to the active metabolite of clopidogrel was reduced by 35% to 40% over this time period. Pharmacodynamic parameters were also measured and demonstrated that the change in inhibition of platelet aggregation was related to the change in the exposure to clopidogrel active metabolite.

Concomitant Use with Mycophenolate Mofetil

Administration of omeprazole 20 mg twice daily for 4 days and a single 1000 mg dose of MMF approximately one hour after the last dose of omeprazole to 12 healthy subjects in a cross-over study resulted in a 52% reduction in the Cmax and 23% reduction in the AUC of MPA.

Specific Populations

Age: Geriatric Population

The AUC and Cmax values were slightly higher (25% and 18%, respectively) in the elderly as compared to younger subjects at steady state. Dosage adjustment based on age is not necessary.

Age: Pediatric Population

1 to 11 Month of Age

The pharmacokinetic parameters following repeated dose administration of 1.0 mg/kg esomeprazole in 1 to 11 month old infants are summarized in Table 5.

Table 5: Summary of PK Parameters in 1 Month to < 1 Year Olds with GERD Following 7/8 Days of Once-Daily Oral Esomeprazole Treatment
 | 1 month to < 1 year
Parameter | 1.0 mg/kg
AUC (μmol·h/L) (n=7) [Geometric mean] | 3.51
Css,,max (μmol/L) (n=15) | 0.87
t½ (hours) (n=8) | 0.93
tmax (hours) (n=15) [Median] | 3.0

Subsequent pharmacokinetic simulation analyses showed that a dosage regimen of 2.5 mg once-daily for pediatric patients with body weight 3 to 5 kg, 5.0 mg once-daily for >5 to 7.5 kg and 10 mg once-daily for >7.5 to 12 kg would achieve comparable steady-state plasma exposures (AUC) to that observed after 10 mg in 1 to 11 year olds, and 20 mg in 12 to 18 year-olds as well as adults.

1 to 11 Years of Age

The pharmacokinetics of esomeprazole were studied in pediatric patients with GERD aged 1 to 11 years. Following once daily dosing for 5 days, the total exposure (AUC) for the 10 mg dose in patients aged 6 to 11 years was similar to that seen with the 20 mg dose in adults and adolescents aged 12 to 17 years. The total exposure for the 10 mg dose in patients aged 1 to 5 years was approximately 30% higher than the 10 mg dose in patients aged 6 to 11 years. The total exposure for the 20 mg dose in patients aged 6 to 11 years was higher than that observed with the 20 mg dose in 12 to 17 year-olds and adults, but lower than that observed with the 40 mg dose in 12 to 17 year-olds and adults. See Table 6.

Table 6: Summary of PK Parameters in 1 to 11 Year Olds with GERD following 5 Days of Once-Daily Oral Esomeprazole Treatment
 | 1 to 5 Year Olds | 6 to 11 Year Olds
Parameter | 10 mg (N=8) | 10 mg (N=7) | 20 mg (N=6)
AUC (μmol·h/L) [Geometric mean] | 4.83 | 3.70 | 6.28
Cmax (μmol/L) | 2.98 | 1.77 | 3.73
tmax (h) [Arithmetic mean] | 1.44 | 1.79 | 1.75
t½λz (h) | 0.74 | 0.88 | 0.73
Cl/F (L/h) | 5.99 | 7.84 | 9.22

12 to 17 Years of Age

The pharmacokinetics of esomeprazole magnesium were studied in 28 adolescent patients with GERD aged 12 to 17 years inclusive, in a single center study. Patients were randomized to receive esomeprazole magnesium 20 mg or 40 mg once daily for 8 days. Mean Cmax and AUC values of esomeprazole were not affected by body weight or age; and more than dose-proportional increases in mean Cmax and AUC values were observed between the two dose groups in the study. Overall, esomeprazole magnesium pharmacokinetics in adolescent patients aged 12 to 17 years were similar to those observed in adult patients with symptomatic GERD. See Table 7.

Table 7: Comparison of PK Parameters in 12 to 17 Year Olds with GERD and Adults with Symptomatic GERD Following the Repeated Daily Oral Dose Administration of Esomeprazole [Duration of treatment for 12 to 17 year olds and adults were 8 days and 5 days, respectively. Data were obtained from two independent studies.]
 | 12 to 17 Year Olds (N=28) |  | Adults (N=36)
 | 20 mg | 40 mg | 20 mg | 40 mg
AUC (μmol·h/L) | 3.65 | 13.86 | 4.2 | 12.6
Cmax (μmol/L) | 1.45 | 5.13 | 2.1 | 4.7
tmax (h) | 2.00 | 1.75 | 1.6 | 1.6
t½λz (h) | 0.82 | 1.22 | 1.2 | 1.5
Data presented are geometric means for AUC, Cmax and t½λz, and median value for tmax.

Gender

The AUC and Cmax values were slightly higher (13%) in females than in males at steady state. Dosage adjustment based on gender is not necessary.

Hepatic Insufficiency

The steady state pharmacokinetics of esomeprazole obtained after administration of 40 mg once daily to 4 patients each with mild (Child-Pugh Class A), moderate (Child-Pugh Class B), and severe (Child-Pugh Class C) liver insufficiency were compared to those obtained in 36 male and female GERD patients with normal liver function. In patients with mild and moderate hepatic insufficiency, the AUCs were within the range that could be expected in patients with normal liver function. In patients with severe hepatic insufficiency the AUCs were 2 to 3 times higher than in the patients with normal liver function. No dosage adjustment is recommended for patients with mild to moderate hepatic insufficiency (Child-Pugh Classes A and B). However, in patients with severe hepatic insufficiency (Child-Pugh Class C) a dose of 20 mg once daily should not be exceeded [see Dosage and Administration (2)].

Renal Insufficiency

The pharmacokinetics of esomeprazole magnesium delayed-release capsules in patients with renal impairment are not expected to be altered relative to healthy volunteers as less than 1% of esomeprazole is excreted unchanged in urine.

Other pharmacokinetic observations

Co-administration of oral contraceptives, diazepam, phenytoin, or quinidine did not seem to change the pharmacokinetic profile of esomeprazole.

Studies evaluating concomitant administration of esomeprazole and either naproxen (non-selective NSAID) or rofecoxib (COX-2 selective NSAID) did not identify any clinically relevant changes in the pharmacokinetic profiles of esomeprazole or these NSAIDs.

12.4 Microbiology

Esomeprazole magnesium, amoxicillin, and clarithromycin triple therapy has been shown to be active against most strains of Helicobacter pylori (H. pylori) in vitro and in clinical infections [see Indications and Usage (1) and Clinical Studies (14)].

Helicobacter pylori: Susceptibility testing of H. pylori isolates was performed for amoxicillin and clarithromycin using agar dilution methodology, and minimum inhibitory concentrations (MICs) were determined.

Pretreatment Resistance: Clarithromycin pretreatment resistance rate (MIC ≥ 1 mcg/mL) to H. pylori was 15% (66/445) at baseline in all treatment groups combined. A total of > 99% (394/395) of patients had H. pylori isolates that were considered to be susceptible (MIC ≤ 0.25 mcg/mL) to amoxicillin at baseline. One patient had a baseline H. pylori isolate with an amoxicillin MIC = 0.5 mcg/mL.

Clarithromycin Susceptibility Test Results and Clinical/Bacteriologic Outcomes: The baseline H. pylori clarithromycin susceptibility results and the H. pylori eradication results at the Day 38 visit are shown in the Table 8:

Table 8: Clarithromycin Susceptibility Test Results and Clinical/Bacteriological Outcomes [Includes only patients with pretreatment and post-treatment clarithromycin susceptibility test results.] for Triple Therapy - (Esomeprazole magnesium 40 mg once daily/amoxicillin 1000 mg twice daily/clarithromycin 500 mg twice daily for 10 days)
Clarithromycin; Pretreatment Results | H. pylori negative; (Eradicated) | H. pylori positive; (Not Eradicated); Post-treatment susceptibility results
 |  | S [Susceptible (S) MIC ≤ 0.25 mcg/mL, Intermediate (I) MIC = 0.5 mcg/mL, Resistant (R) MIC ≥ 1.0 mcg/mL.] | I | R | No MIC
Susceptible 182 | 162 | 4 | 0 | 2 | 14
Intermediate 1 | 1 | 0 | 0 | 0 | 0
Resistant 29 | 13 | 1 | 0 | 13 | 2

Patients not eradicated of H. pylori following esomeprazole magnesium/amoxicillin/clarithromycin triple therapy will likely have clarithromycin resistant H. pylori isolates. Therefore, clarithromycin susceptibility testing should be done, when possible. Patients with clarithromycin resistant H. pylori should not be re-treated with a clarithromycin-containing regimen.

Amoxicillin Susceptibility Test Results and Clinical/Bacteriological Outcomes:

In the esomeprazole magnesium/amoxicillin/clarithromycin clinical trials, 83% (176/212) of the patients in the esomeprazole magnesium/amoxicillin/clarithromycin treatment group who had pretreatment amoxicillin susceptible MICs (≤ 0.25 mcg/mL) were eradicated of H. pylori, and 17% (36/212) were not eradicated of H. pylori. Of the 36 patients who were not eradicated of H. pylori on triple therapy, 16 had no post-treatment susceptibility test results and 20 had post-treatment H. pylori isolates with amoxicillin susceptible MICs. Fifteen of the patients who were not eradicated of H. pylori on triple therapy also had post-treatment H. pylori isolates with clarithromycin resistant MICs. There were no patients with H. pylori isolates who developed treatment emergent resistance to amoxicillin.

Susceptibility Test for Helicobacter pylori: For susceptibility testing information about Helicobacter pylori, see Microbiology section in prescribing information for clarithromycin and amoxicillin.

Effects on Gastrointestinal Microbial Ecology: Decreased gastric acidity due to any means, including proton pump inhibitors, increases gastric counts of bacteria normally present in the gastrointestinal tract. Treatment with proton pump inhibitors may lead to slightly increased risk of gastrointestinal infections such as Salmonella and Campylobacter and possibly Clostridium difficile in hospitalized patients.

13 NONCLINICAL TOXICOLOGY

13.1 Carcinogenesis, Mutagenesis, Impairment of Fertility

The carcinogenic potential of esomeprazole magnesium was assessed using studies of omeprazole, of which esomeprazole is an enantiomer. In two 24-month oral carcinogenicity studies in rats, omeprazole at daily doses of 1.7, 3.4, 13.8, 44, and 140.8 mg/kg/day (about 0.4 to 34 times the human dose of 40 mg/day expressed on a body surface area basis) produced gastric ECL cell carcinoids in a dose-related manner in both male and female rats; the incidence of this effect was markedly higher in female rats, which had higher blood levels of omeprazole. Gastric carcinoids seldom occur in the untreated rat. In addition, ECL cell hyperplasia was present in all treated groups of both sexes. In one of these studies, female rats were treated with 13.8 mg omeprazole/kg/day (about 3.4 times the human dose of 40 mg/day on a body surface area basis) for 1 year, then followed for an additional year without the drug. No carcinoids were seen in these rats. An increased incidence of treatment-related ECL cell hyperplasia was observed at the end of 1 year (94% treated vs. 10% controls). By the second year the difference between treated and control rats was much smaller (46% vs. 26%) but still showed more hyperplasia in the treated group. Gastric adenocarcinoma was seen in one rat (2%). No similar tumor was seen in male or female rats treated for 2 years. For this strain of rat no similar tumor has been noted historically, but a finding involving only one tumor is difficult to interpret. A 78-week mouse carcinogenicity study of omeprazole did not show increased tumor occurrence, but the study was not conclusive.

Esomeprazole was negative in the Ames mutation test, in the in vivo rat bone marrow cell chromosome aberration test, and the in vivo mouse micronucleus test. Esomeprazole, however, was positive in the in vitro human lymphocyte chromosome aberration test. Omeprazole was positive in the in vitro human lymphocyte chromosome aberration test, the in vivo mouse bone marrow cell chromosome aberration test, and the in vivo mouse micronucleus test.

The potential effects of esomeprazole on fertility and reproductive performance were assessed using omeprazole studies. Omeprazole at oral doses up to 138 mg/kg/day in rats (about 34 times the human dose of 40 mg/day on a body surface area basis) was found to have no effect on reproductive performance of parental animals.

13.2 Animal Toxicology and/or Pharmacology

Reproduction Studies

Reproduction studies have been performed in rats at oral doses up to 280 mg/kg/day (about 68 times an oral human dose of 40 mg on a body surface area basis) and in rabbits at oral doses up to 86 mg/kg/day (about 42 times an oral human dose of 40 mg on a body surface area basis) and have revealed no evidence of impaired fertility or harm to the fetus due to esomeprazole [see Use in Specific Populations (8.1)].

Juvenile Animal Study

A 28-day toxicity study with a 14-day recovery phase was conducted in juvenile rats with esomeprazole magnesium at doses of 70 to 280 mg /kg/day (about 17 to 68 times a daily oral human dose of 40 mg on a body surface area basis). An increase in the number of deaths at the high dose of 280 mg/kg/day was observed when juvenile rats were administered esomeprazole magnesium from postnatal day 7 through postnatal day 35. In addition, doses equal to or greater than 140 mg/kg/day (about 34 times a daily oral human dose of 40 mg on a body surface area basis), produced treatment-related decreases in body weight (approximately 14%) and body weight gain, decreases in femur weight and femur length, and affected overall growth. Comparable findings described above have also been observed in this study with another esomeprazole salt, esomeprazole strontium, at equimolar doses of esomeprazole.

14 CLINICAL STUDIES

14.1 Healing of Erosive Esophagitis

The healing rates of esomeprazole magnesium 40 mg, esomeprazole magnesium 20 mg, and omeprazole 20 mg (the approved dose for this indication) were evaluated in patients with endoscopically diagnosed erosive esophagitis in four multicenter, double-blind, randomized studies. The healing rates at Weeks 4 and 8 were evaluated and are shown in the Table 9:

Table 9: Erosive Esophagitis Healing Rate (Life-Table Analysis)
Study | No. of Patients | Treatment Groups | Week 4 |  | Week 8 | Significance Level [log-rank test vs. omeprazole 20 mg]
1 | 588 | Esomeprazole Magnesium 20 mg |  | 68.7% | 90.6% | N.S. [N.S. = not significant (p > 0.05)]
 | 588 | Omeprazole 20 mg |  | 69.5% | 88.3%
2 | 654 | Esomeprazole Magnesium 40 mg |  | 75.9% | 94.1% | p < 0.001
 | 656 | Esomeprazole Magnesium 20 mg |  | 70.5% | 89.9% | p < 0.05
 | 650 | Omeprazole 20 mg |  | 64.7% | 86.9%
3 | 576 | Esomeprazole Magnesium 40 mg |  | 71.5% | 92.2% | N.S.
 | 572 | Omeprazole 20 mg |  | 68.6% | 89.8%
4 | 1216 | Esomeprazole Magnesium 40 mg |  | 81.7% | 93.7% | p < 0.001
 | 1209 | Omeprazole 20 mg |  | 68.7% | 84.2%

In these same studies of patients with erosive esophagitis, sustained heartburn resolution and time to sustained heartburn resolution were evaluated and are shown in the Table 10:

Table 10: Sustained Resolution [Defined as 7 consecutive days with no heartburn reported in daily patient diary.] of Heartburn (Erosive Esophagitis Patients)
 |  |  | Cumulative Percent [Defined as the cumulative proportion of patients who have reached the start of sustained resolution.] with Sustained Resolution
Study | No. of Patients | Treatment Groups | Day 14 | Day 28 | Significance Level [log-rank test vs. omeprazole 20 mg.]
1 | 573 | Esomeprazole Magnesium 20 mg | 64.3% | 72.7% | N.S. [N.S. = not significant (p > 0.05)]
 | 555 | Omeprazole 20 mg | 64.1% | 70.9%
2 | 621 | Esomeprazole Magnesium 40 mg | 64.8% | 74.2% | p <0.001
 | 620 | Esomeprazole Magnesium 20 mg | 62.9% | 70.1% | N.S.
 | 626 | Omeprazole 20 mg | 56.5% | 66.6%
3 | 568 | Esomeprazole Magnesium 40 mg | 65.4% | 73.9% | N.S.
 | 551 | Omeprazole 20 mg | 65.5% | 73.1%
4 | 1187 | Esomeprazole Magnesium 40 mg | 67.6% | 75.1% | p <0.001
 | 1188 | Omeprazole 20 mg | 62.5% | 70.8%

In these four studies, the range of median days to the start of sustained resolution (defined as 7 consecutive days with no heartburn) was 5 days for esomeprazole magnesium 40 mg, 7 to 8 days for esomeprazole magnesium 20 mg and 7 to 9 days for omeprazole 20 mg.

There are no comparisons of 40 mg of esomeprazole magnesium with 40 mg of omeprazole in clinical trials assessing either healing or symptomatic relief of erosive esophagitis.

Long-Term Maintenance of Healing of Erosive Esophagitis

Two multicenter, randomized, double-blind placebo-controlled 4-arm trials were conducted in patients with endoscopically confirmed, healed erosive esophagitis to evaluate esomeprazole magnesium 40 mg (n=174), 20 mg (n=180), 10 mg (n=168) or placebo (n=171) once daily over six months of treatment.

No additional clinical benefit was seen with esomeprazole magnesium 40 mg over esomeprazole magnesium 20 mg.

The percentages of patients that maintained healing of erosive esophagitis at the various time points are shown in the Figures 2 and 3:

s= scheduled visit

s= scheduled visit

Patients remained in remission significantly longer and the number of recurrences of erosive esophagitis was significantly less in patients treated with esomeprazole magnesium compared to placebo.

In both studies, the proportion of patients on esomeprazole magnesium who remained in remission and were free of heartburn and other GERD symptoms was well differentiated from placebo.

In a third multicenter open label study of 808 patients treated for 12 months with esomeprazole magnesium 40 mg, the percentage of patients that maintained healing of erosive esophagitis was 93.7% for six months and 89.4% for one year.

14.2 Symptomatic Gastroesophageal Reflux Disease (GERD)

Two multicenter, randomized, double-blind, placebo-controlled studies were conducted in a total of 717 patients comparing four weeks of treatment with esomeprazole magnesium 20 mg or 40 mg once daily versus placebo for resolution of GERD symptoms. Patients had ≥ 6-month history of heartburn episodes, no erosive esophagitis by endoscopy, and heartburn on at least four of the seven days immediately preceding randomization.

The percentage of patients that were symptom-free of heartburn was significantly higher in the esomeprazole magnesium groups compared to placebo at all follow-up visits (Weeks 1, 2, and 4).

No additional clinical benefit was seen with esomeprazole magnesium 40 mg over esomeprazole magnesium 20 mg.

The percent of patients symptom-free of heartburn by day are shown in the Figures 4 and 5:

In three European symptomatic GERD trials, esomeprazole magnesium 20 mg and 40 mg and omeprazole 20 mg were evaluated. No significant treatment related differences were seen.

14.3 Pediatric Gastroesophageal Reflux Disease (GERD)

1 to 11 Years of Age

In a multicenter, parallel-group study, 109 pediatric patients with a history of endoscopically-proven GERD (1 to 11 years of age; 53 female; 89 Caucasian, 19 Black, 1 Other) were treated with esomeprazole magnesium once daily for up to 8 weeks to evaluate safety and tolerability. Dosing by patient weight was as follows:

weight < 20 kg: once daily treatment with esomeprazole magnesium 5 mg or 10 mg
weight ≥ 20 kg: once daily treatment with esomeprazole magnesium 10 mg or 20 mg

Patients were endoscopically characterized as to the presence or absence of erosive esophagitis.

Of the 109 patients, 53 had erosive esophagitis at baseline (51 had mild, 1 moderate, and 1 severe esophagitis). Although most of the patients who had a follow-up endoscopy at the end of 8 weeks of treatment healed, spontaneous healing cannot be ruled out because these patients had low grade erosive esophagitis prior to treatment, and the trial did not include a concomitant control.

12 to 17 Years of Age

In a multicenter, randomized, double-blind, parallel-group study, 149 adolescent patients (12 to 17 years of age; 89 female; 124 Caucasian, 15 Black, 10 Other) with clinically diagnosed GERD were treated with either esomeprazole magnesium 20 mg or 40 mg once daily for up to 8 weeks to evaluate safety and tolerability. Patients were not endoscopically characterized as to the presence or absence of erosive esophagitis.

14.4 Risk Reduction of NSAID-Associated Gastric Ulcer

Two multicenter, double-blind, placebo-controlled studies were conducted in patients at risk of developing gastric and/or duodenal ulcers associated with continuous use of non-selective and COX-2 selective NSAIDs. A total of 1429 patients were randomized across the 2 studies. Patients ranged in age from 19 to 89 (median age 66.0 years) with 70.7% female, 29.3% male, 82.9% Caucasian, 5.5% Black, 3.7% Asian, and 8.0% Others. At baseline, the patients in these studies were endoscopically confirmed not to have ulcers but were determined to be at risk for ulcer occurrence due to their age (≥60 years) and/or history of a documented gastric or duodenal ulcer within the past 5 years. Patients receiving NSAIDs and treated with esomeprazole magnesium 20 mg or 40 mg once-a-day experienced significant reduction in gastric ulcer occurrences relative to placebo treatment at 26 weeks. See Table 11. No additional benefit was seen with esomeprazole magnesium 40 mg over 20 mg. These studies did not demonstrate significant reduction in the development of NSAID-associated duodenal ulcer due to the low incidence.

Table 11: Cumulative Percentage of Patients without Gastric Ulcers at 26 Weeks
Study | No. of Patients | Treatment Group | % of Patients Remaining Gastric Ulcer Free [%= Life Table Estimate. Significant difference from placebo (p<0.01).]
1 | 191; 194; 184 | Esomeprazole Magnesium 20 mg; Esomeprazole Magnesium 40 mg; Placebo | 95.4; 96.7; 88.2
2 | 267; 271; 257 | Esomeprazole Magnesium 20 mg; Esomeprazole Magnesium 40 mg; Placebo | 94.7; 95.3; 83.3

14.5 Helicobacter pylori (H. pylori) Eradication in Patients with Duodenal Ulcer Disease

Triple Therapy (esomeprazole magnesium/amoxicillin/clarithromycin): Two multicenter, randomized, double-blind studies were conducted using a 10 day treatment regimen. The first study (191) compared esomeprazole magnesium 40 mg once daily in combination with amoxicillin 1000 mg twice daily and clarithromycin 500 mg twice daily to esomeprazole magnesium 40 mg once daily plus clarithromycin 500 mg twice daily. The second study (193) compared esomeprazole magnesium 40 mg once daily in combination with amoxicillin 1000 mg twice daily and clarithromycin 500 mg twice daily to esomeprazole magnesium 40 mg once daily. H. pylori eradication rates, defined as at least two negative tests and no positive tests from CLOtest®, histology and/or culture, at 4 weeks post-therapy were significantly higher in the esomeprazole magnesium plus amoxicillin and clarithromycin group than in the esomeprazole magnesium plus clarithromycin or esomeprazole magnesium alone group. The results are shown in Table 12:

Table 12: H. pylori Eradication Rates at 4 Weeks after 10 Day Treatment Regimen % of Patients Cured [95% Confidence Interval] (Number of Patients)
Study | Treatment Group | Per-Protocol [Patients were included in the analysis if they had H. pylori infection documented at baseline, had at least one endoscopically verified duodenal ulcer ≥ 0.5 cm in diameter at baseline or had a documented history of duodenal ulcer disease within the past 5 years, and were not protocol violators. Patients who dropped out of the study due to an adverse reaction related to the study drug were included in the analysis as not H. pylori eradicated.] | Intent-to-Treat [Patients were included in the analysis if they had documented H. pylori infection at baseline, had at least one documented duodenal ulcer at baseline, or had a documented history of duodenal ulcer disease, and took at least one dose of study medication. All dropouts were included as not H. pylori eradicated.]
191 | Esomeprazole magnesium plus amoxicillin and clarithromycin | 84% [p < 0.05 compared to esomeprazole magnesium plus clarithromycin.]; [78, 89]; (n=196) | 77%; [71, 82]; (n=233)
 | Esomeprazole magnesium plus clarithromycin | 55%; [48, 62]; (n=187) | 52%; [45, 59]; (n=215)
193 | Esomeprazole magnesium plus amoxicillin and clarithromycin | 85% [p < 0.05 compared to esomeprazole magnesium alone.]; [74, 93]; (n=67) | 78%; [67, 87]; (n=74)
 | Esomeprazole magnesium | 5%; [0, 23]; (n=22) | 4%; [0, 21]; (n=24)

The percentage of patients with a healed baseline duodenal ulcer by 4 weeks after the 10 day treatment regimen in the esomeprazole magnesium plus amoxicillin and clarithromycin group was 75% (n=156) and 57% (n=60) respectively, in the 191 and 193 studies (per-protocol analysis).

14.6 Pathological Hypersecretory Conditions Including Zollinger-Ellison Syndrome

In a multicenter, open-label dose-escalation study of 21 patients (15 males and 6 females, 18 Caucasian and 3 Black, mean age of 55.5 years) with pathological hypersecretory conditions, such as Zollinger-Ellison Syndrome, esomeprazole magnesium significantly inhibited gastric acid secretion. Initial dose was 40 mg twice daily in 19/21 patients and 80 mg twice daily in 2/21 patients. Total daily doses ranging from 80 mg to 240 mg for 12 months maintained gastric acid output below the target levels of 10 mEq/h in patients without prior gastric acid-reducing surgery and below 5 mEq/hr in patients with prior gastric acid-reducing surgery. At the Month 12 final visit, 18/20 (90%) patients had Basal Acid Output (BAO) under satisfactory control (median BAO = 0.17 mmol/hr). Of the 18 patients evaluated with a starting dose of 40 mg twice daily, 13 (72%) had their BAO controlled with the original dosing regimen at the final visit. See Table 13.

Table 13: Adequate Acid Suppression at Final Visit by Dose Regimen
Esomeprazole Magnesium dose at the Month 12 visit | BAO under adequate control at the Month 12 visit (N=20) [One patient was not evaluated.]
40 mg twice daily | 13/15
80 mg twice daily | 4/4
80 mg three times daily | 1/1

16 HOW SUPPLIED/STORAGE AND HANDLING

Product: 50090-4639

NDC: 50090-4639-0 30 CAPSULE, DELAYED RELEASE in a BOTTLE

NDC: 50090-4639-1 90 CAPSULE, DELAYED RELEASE in a BOTTLE

17 PATIENT COUNSELING INFORMATION

Advise the patient to read the FDA-approved patient labeling (Medication Guide).

Adverse Reactions

Advise patients to report to their healthcare provider if they experience any signs or symptoms consistent with:

- Hypersensitivity Reactions [see Contraindications (4)]
- Acute Tubulointerstitial Nephritis [see Warnings and Precautions (5.2)]
- Clostridium difficile-Associated Diarrhea [see Warnings and Precautions (5.3)]
- Bone Fracture [see Warnings and Precaution (5.4)]
- Cutaneous and Systemic Lupus Erythematosus [see Warnings and Precautions (5.5)]
- Cyanocobalamin (Vitamin B-12) Deficiency [see Warnings and Precautions (5.7)]
- Hypomagnesemia [see Warnings and Precautions (5.8)]

Drug Interactions

- Advise patients to let you know if they are taking, or begin taking, other medications, because esomeprazole magnesium delayed-release capsules can interfere with antiretroviral drugs and drugs that are affected by gastric pH changes [see Drug Interactions (7.1)].

Administration

- Let patients know that antacids may be used while taking esomeprazole magnesium delayed-release capsules.
- Advise patients to take esomeprazole magnesium delayed-release capsules at least one hour before a meal.
- For patients who are prescribed esomeprazole magnesium delayed-release capsules, advise them not to chew or crush the capsules.
- Advise patients that, if they open esomeprazole magnesium delayed-release capsules to mix the granules with food, the granules should only be mixed with applesauce. Use with other foods has not been evaluated and is not recommended.
- For patients who are advised to open the esomeprazole magnesium delayed-release capsules before taking them, instruct them in the proper technique for administration [see Dosage and Administration (2)] and tell them to follow the dosing instructions in the PATIENT INFORMATION insert included in the package. Instruct patients to rinse the syringe with water after each use.

Distributed by:

AstraZeneca Pharmaceuticals LP

Wilmington, DE 19850

MEDICATION GUIDE

ESOMEPRAZOLE MAGNESIUM

Delayed-Release Capsules

Read the Medication Guide that comes with esomeprazole magnesium delayed-release capsules before you start taking esomeprazole magnesium delayed-release capsules and each time you get a refill. There may be new information. This information does not take the place of talking with your doctor about your medical condition or your treatment.

What is the most important information I should know about esomeprazole magnesium delayed-release capsules?

Esomeprazole magnesium delayed-release capsules may help your acid-related symptoms, but you could still have serious stomach problems. Talk with your doctor.

Esomeprazole magnesium delayed-release capsules can cause serious side effects, including:

- A type of kidney problem (acute tubulointerstitial nephritis). Some people who take proton pump inhibitor (PPI) medicines, including esomeprazole magnesium delayed-release capsules, may develop a kidney problem called acute tubulointerstitial nephritis that can happen at any time during treatment with esomeprazole magnesium delayed-release capsules. Call your doctor if you have a decrease in the amount that you urinate or if you have blood in your urine.

- Diarrhea. Esomeprazole magnesium delayed-release capsules may increase your risk of getting severe diarrhea. This diarrhea may be caused by an infection (Clostridium difficile) in your intestines.
  Call your doctor right away if you have watery stool, stomach pain, and fever that does not go away.

- Bone fractures. People who take multiple daily doses of PPI medicines for a long period of time (a year or longer) may have an increased risk of fractures of the hip, wrist, or spine. You should take esomeprazole magnesium delayed-release capsules exactly as prescribed, at the lowest dose possible for your treatment and for the shortest time needed. Talk to your doctor about your risk of bone fracture if you take esomeprazole magnesium delayed-release capsules.

- Certain types of lupus erythematosus. Lupus erythematosus is an autoimmune disorder (the body’s immune cells attack other cells or organs in the body). Some people who take PPI medicines, including esomeprazole magnesium delayed-release capsules, may develop certain types of lupus erythematosus or have worsening of the lupus they already have. Call your doctor right away if you have new or worsening joint pain or a rash on your cheeks or arms that gets worse in the sun.

Esomeprazole magnesium delayed-release capsules can have other serious side effects. See “What are the possible side effects of esomeprazole magnesium delayed-release capsules?”

What are esomeprazole magnesium delayed-release capsules?

Esomeprazole magnesium delayed-release capsules are a prescription medicine called a proton pump inhibitor (PPI). Esomeprazole magnesium delayed-release capsules reduce the amount of acid in your stomach.

Esomeprazole magnesium delayed-release capsules are used in adults:

- for 4 to 8 weeks to treat the symptoms of gastroesophageal reflux disease (GERD). Esomeprazole magnesium delayed-release capsules may also be prescribed to heal acid-related damage to the lining of the esophagus (erosive esophagitis), and to help continue this healing.
  GERD happens when acid in your stomach backs up into the tube (esophagus) that connects your mouth to your stomach. This may cause a burning feeling in your chest or throat, sour taste, or burping.

- for up to 6 months to reduce the risk of stomach ulcers in some people taking pain medicines called non-steroidal anti-inflammatory drugs (NSAIDs).

- to treat patients with a stomach infection (Helicobacter pylori), along with the antibiotics amoxicillin and clarithromycin.

- for the long-term treatment of conditions where your stomach makes too much acid, including Zollinger-Ellison Syndrome. Zollinger-Ellison Syndrome is a rare condition in which the stomach produces a more than normal amount of acid.

For children and adolescents 1 year to 17 years of age, esomeprazole magnesium delayed-release capsules may be prescribed for up to 8 weeks for short-term treatment of GERD.

In children ages 1 month to less than 1 year of age, esomeprazole magnesium delayed-release capsules are only used to treat GERD with acid-related damage to the esophagus (erosive esophagitis) for up to 6 weeks.

It is not known if esomeprazole magnesium delayed-release capsules are effective in children under 1 month of age.

Who should not take esomeprazole magnesium delayed-release capsules?

Do not take esomeprazole magnesium delayed-release capsules if you:

- are allergic to esomeprazole magnesium or any of the ingredients in esomeprazole magnesium delayed-release capsules. See the end of this Medication Guide for a complete list of ingredients in esomeprazole magnesium delayed-release capsules.

- are allergic to any other PPI medicine.

What should I tell my doctor before taking esomeprazole magnesium delayed-release capsules?

Before you take esomeprazole magnesium delayed-release capsules, tell your doctor if you:

- have been told that you have low magnesium levels in your blood.

- have liver problems.

- are pregnant or plan to become pregnant. It is not known if esomeprazole magnesium delayed-release capsules can harm your unborn baby.

- are breastfeeding or planning to breastfeed. Esomeprazole magnesium delayed-release capsules may pass into your breast milk. Talk to your doctor about the best way to feed your baby if you take esomeprazole magnesium delayed-release capsules.

Tell your doctor about all of the medicines you take, including prescription and non-prescription drugs, vitamins and herbal supplements. Esomeprazole magnesium delayed-release capsules may affect how other medicines work, and other medicines may affect how esomeprazole magnesium delayed-release capsules work.

Especially tell your doctor if you take:

- warfarin (Coumadin, Jantoven)
- ketoconazole (Nizoral)
- voriconazole (Vfend)
- atazanavir (Reyataz)
- nelfinavir (Viracept)
- saquinavir (Fortovase)
- products that contain iron
- digoxin (Lanoxin)
- St. John’s Wort (Hypericum perforatum)

- Rifampin (Rimactane, Rifater, Rifamate)
- cilostazol (Pletal)
- diazepam (Valium)
- tacrolimus (Prograf)
- erlotinib (Tarceva)
- methotrexate
- clopidogrel (Plavix)
- mycophenolate mofetil (Cellcept)

How should I take esomeprazole magnesium delayed-release capsules?

- Take esomeprazole magnesium delayed-release capsules exactly as prescribed by your doctor.
- Do not change your dose or stop esomeprazole magnesium delayed-release capsules without talking to your doctor.
- Take esomeprazole magnesium delayed-release capsules at least 1 hour before a meal.
- Swallow esomeprazole magnesium delayed-release capsules whole. Never chew or crush esomeprazole magnesium delayed-release capsules.
- If you have difficulty swallowing esomeprazole magnesium delayed-release capsules, you may open the capsule and empty the contents into a tablespoon of applesauce. Do not crush or chew the granules. Be sure to swallow the applesauce right away. Do not store it for later use.
- If you forget to take a dose of esomeprazole magnesium delayed-release capsules, take it as soon as you remember. If it is almost time for your next dose, do not take the missed dose. Take the next dose on time. Do not take a double dose to make up for a missed dose.
- If you take too many esomeprazole magnesium delayed-release capsules, call your doctor or local poison control center right away, or go to the nearest hospital emergency room.
- See the “Instructions for Use” at the end of this Medication Guide for instructions how to mix and give esomeprazole magnesium delayed-release capsules through a nasogastric tube or gastric tube.

What are the possible side effects of esomeprazole magnesium delayed-release capsules?

Esomeprazole magnesium delayed-release capsules can cause serious side effects, including:

- See “What is the most important information I should know about esomeprazole magnesium delayed-release capsules?”
- Vitamin B-12 deficiency. Esomeprazole magnesium delayed-release capsules reduce the amount of acid in your stomach. Stomach acid is needed to absorb vitamin B-12 properly. Talk with your doctor about the possibility of vitamin B-12 deficiency if you have been on esomeprazole magnesium delayed-release capsules for a long time (more than 3 years).
- Low magnesium levels in your body. Low magnesium can happen in some people who take a PPI medicine for at least 3 months. If low magnesium levels happen, it is usually after a year of treatment.

You may or may not have symptoms of low magnesium. Tell your doctor right away if you have any of these symptoms:

  ∘ seizures
  ∘ dizziness
  ∘ abnormal or fast heart beat
  ∘ jitteriness
  ∘ jerking movements or shaking (tremors)

∘ muscle weakness
∘ spasms of the hands and feet
∘ cramps or muscle aches
∘ spasm of the voice box

Your doctor may check the level of magnesium in your body before you start taking esomeprazole magnesium delayed-release capsules or during treatment if you will be taking esomeprazole magnesium delayed-release capsules for a long period of time.

- Stomach growths (fundic gland polyps). People who take PPI medicines for a long time have an increased risk of developing a certain type of stomach growths called fundic gland polyps, especially after taking PPI medicines for more than 1 year.

The most common side effects with esomeprazole magnesium delayed-release capsules may include:

  ∘ headache
  ∘ diarrhea
  ∘ nausea
  ∘ gas

∘ abdominal pain
∘ constipation
∘ dry mouth
∘ drowsiness

Other side effects:

Serious allergic reactions. Tell your doctor if you get any of the following symptoms with esomeprazole magnesium delayed-release capsules:

- rash
- face swelling

- throat tightness
- difficulty breathing

Your doctor may stop esomeprazole magnesium delayed-release capsules if these symptoms happen.

Tell your doctor if you have any side effects that bother you or that do not go away. These are not all the possible side effects with esomeprazole magnesium delayed-release capsules.

Call your doctor for medical advice about side effects. You may report side effects to FDA at 1-800-FDA-1088.

How should I store esomeprazole magnesium delayed-release capsules?

- Store esomeprazole magnesium delayed-release capsules at room temperature between 68°F to 77°F (20°C to 25°C).
- Keep the container of esomeprazole magnesium delayed-release capsules closed tightly.

Keep esomeprazole magnesium delayed-release capsules and all medicines out of the reach of children.

General information about esomeprazole magnesium delayed-release capsules

Medicines are sometimes prescribed for purposes other than those listed in a Medication Guide. Do not use esomeprazole magnesium delayed-release capsules for a condition for which it was not prescribed. Do not give esomeprazole magnesium delayed-release capsules to other people, even if they have the same symptoms you have. They may harm them.

This Medication Guide summarizes the most important information about esomeprazole magnesium delayed-release capsules. If you would like more information, talk with your doctor. You can ask your pharmacist or doctor for information about esomeprazole magnesium delayed-release capsules that is written for health professionals.

For more information, go to www.purplepill.com or call 1-800-463-9486.

What are the ingredients in esomeprazole magnesium delayed-release capsules?

Active ingredient: esomeprazole magnesium trihydrate

Inactive ingredients in esomeprazole magnesium delayed-release capsules (including the capsule shells): glyceryl monostearate 40-55, hydroxypropyl cellulose, hypromellose, magnesium stearate, methacrylic acid copolymer type C, polysorbate 80, sugar spheres, talc, triethyl citrate, gelatin, FD&C Blue #1, FD&C Red #40, titanium dioxide, shellac, ethyl alcohol, isopropyl alcohol, n-butyl alcohol, propylene glycol, sodium hydroxide, polyvinyl pyrrolidone, and TekPrint SW-9008 black ink.

Instructions for Use

For instructions on taking delayed-release capsules, see the section of this leaflet called “How should I take esomeprazole magnesium delayed-release capsules?”

Esomeprazole magnesium delayed-release capsules may be given through a nasogastric tube (NG tube) or gastric tube, as prescribed by your doctor. Follow the instructions below:

Esomeprazole magnesium delayed-release capsules:

- Open the capsule and empty the granules into a 60 mL catheter tipped syringe. Mix with 50 mL of water. Use only a catheter tipped syringe to give esomeprazole magnesium delayed-release capsules through a NG tube.
- Replace the plunger and shake the syringe well for 15 seconds. Hold the syringe with the tip up and check for granules in the tip.
- Give the medicine right away.
- Do not give the granules if they have dissolved or have broken into pieces.
- Attach the syringe to the NG tube. Give the medicine in the syringe through the NG tube into the stomach.
- After giving the granules, flush the NG tube with more water.

This Medication Guide has been approved by the U.S. Food and Drug Administration.

AstraZeneca Pharmaceuticals LP

Wilmington, DE 19850

Revised 11/2020